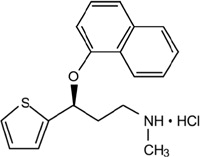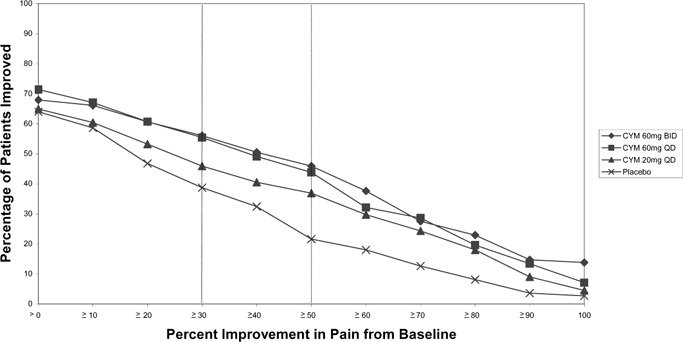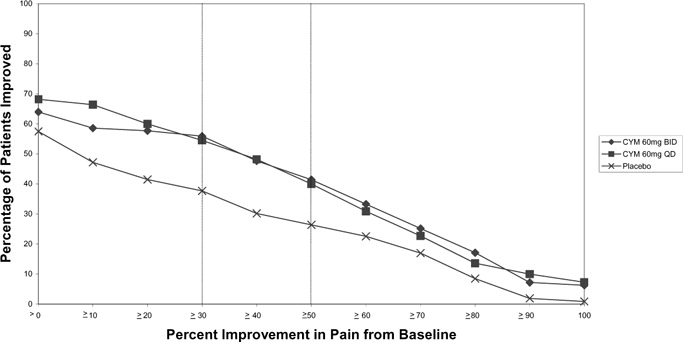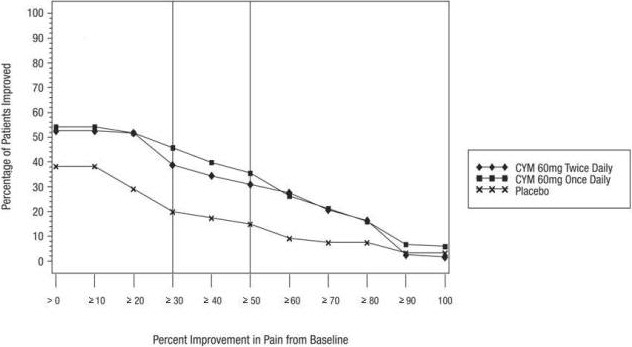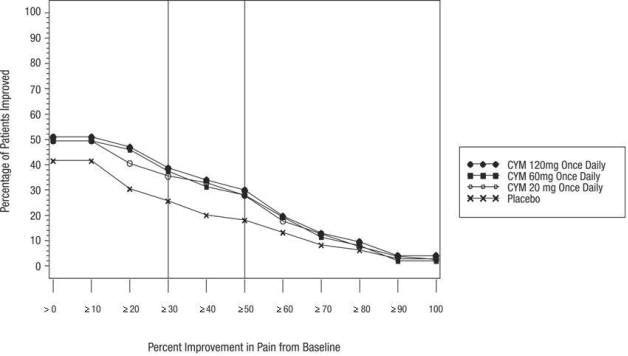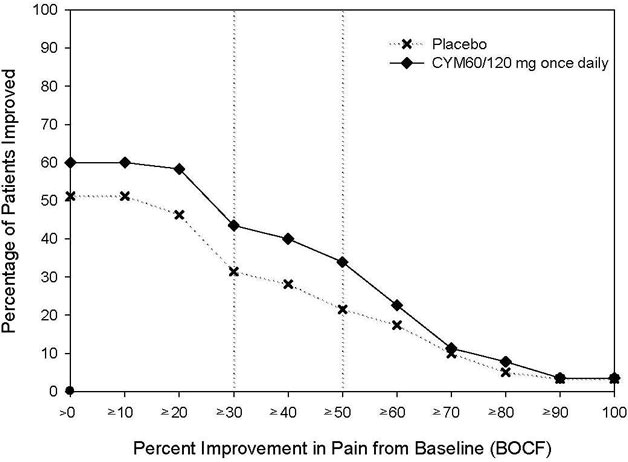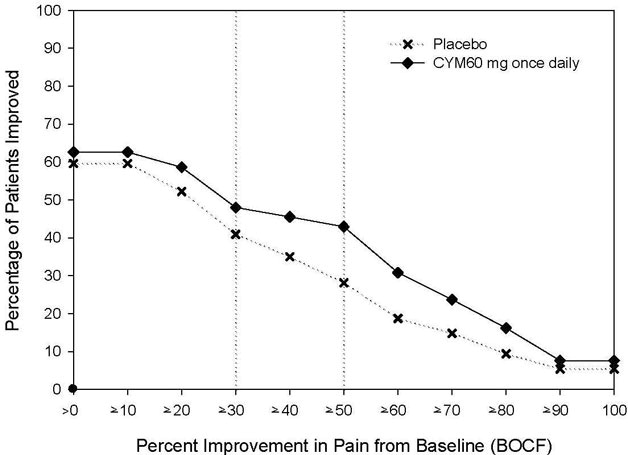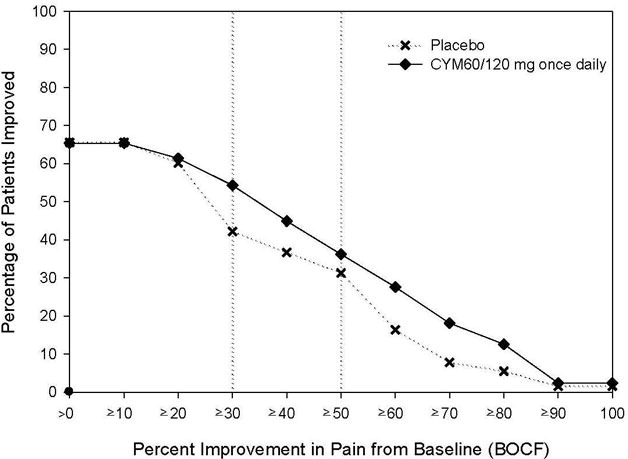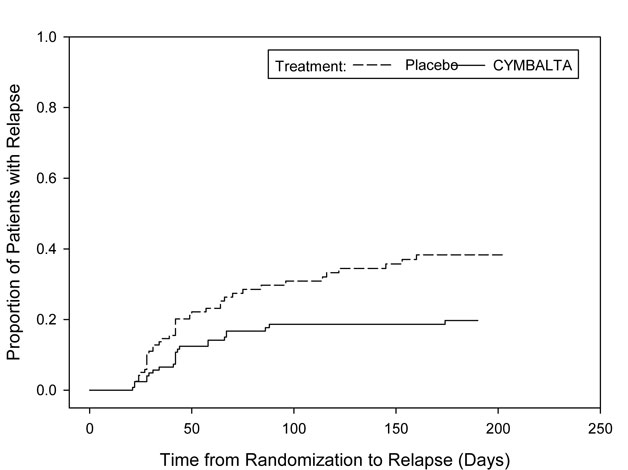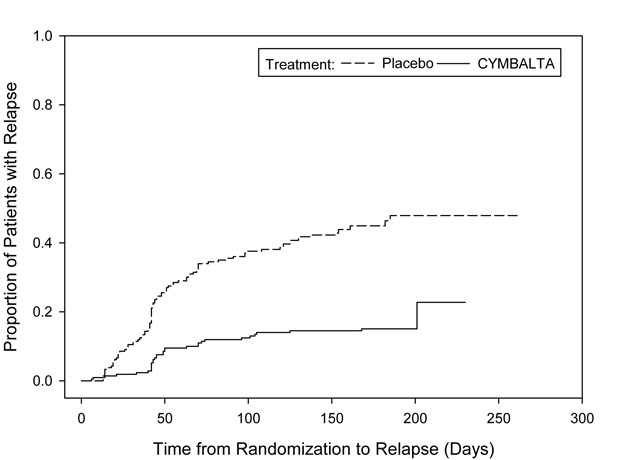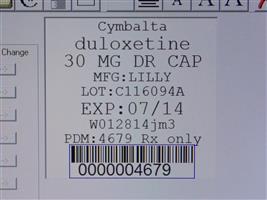 DRUG LABEL: Cymbalta
NDC: 68151-4679 | Form: CAPSULE, DELAYED RELEASE
Manufacturer: Carilion Materials Management
Category: prescription | Type: HUMAN PRESCRIPTION DRUG LABEL
Date: 20160806

ACTIVE INGREDIENTS: DULOXETINE HYDROCHLORIDE 30 mg/1 1
INACTIVE INGREDIENTS: Gelatin; Hypromelloses; HYPROMELLOSE ACETATE SUCCINATE 16070722 (3 MM2/S); Sodium lauryl sulfate; Sucrose; Talc; Titanium dioxide; Triethyl citrate; FD&C BLUE NO. 2

HIGHLIGHTS OF PRESCRIBING INFORMATION

These highlights do not include all the information needed to use CYMBALTA safely and effectively. See full prescribing information for CYMBALTA.
CYMBALTA (Duloxetine Delayed-Release Capsules) for Oral Use.
Initial U.S. Approval: 2004

RECENT MAJOR CHANGES

Boxed Warning: Suicidal Thoughts and Behaviors |  | 10/2014
Indications and Usage (1) |  | 10/2014
Dosage and Administration:
 | Dosage for Treatment of Generalized Anxiety Disorder (2.2) | 10/2014
Contraindications:
 | Uncontrolled Narrow-Angle Glaucoma (4.2) Removed | 07/2014
Warnings and Precautions:
 | Orthostatic Hypotension, Falls and Syncope (5.3) | 11/2014
 | Angle-Closure Glaucoma (5.9) | 07/2014

WARNING: SUICIDAL THOUGHTS AND BEHAVIORS

WARNING: SUICIDALTHOUGHTS AND BEHAVIORS

See full prescribing information for complete boxed warning.

- Increased risk of suicidal thinking and behavior in children, adolescents, and young adults taking antidepressants (5.1)
- Monitor for worsening and emergence of suicidal thoughts and behaviors (5.1)

1 INDICATIONS AND USAGE

CYMBALTA® is a serotonin and norepinephrine reuptake inhibitor (SNRI) indicated for:

- Major Depressive Disorder (MDD) (1)
- Generalized Anxiety Disorder (GAD) (1)
- Diabetic Peripheral Neuropathic Pain (DPNP) (1)
- Fibromyalgia (FM) (1)
- Chronic Musculoskeletal Pain (1)

2 DOSAGE AND ADMINISTRATION

- Take CYMBALTA once daily, with or without food. Swallow CYMBALTA whole; do not crush or chew, do not open capsule. Take a missed dose as soon as it is remembered. Do not take two doses of CYMBALTA at the same time. (2)

Indication | Starting Dose | Target Dose | Maximum Dose
MDD (2.1) | 40 mg/day to 60 mg/day | Acute Treatment: 40 mg/day (20 mg twice daily) to 60 mg/day (once daily or as 30 mg twice daily); Maintenance Treatment: 60 mg/day | 120 mg/day
GAD (2.2)
Adults | 60 mg/day | 60 mg/day (once daily) | 120 mg/day
Elderly | 30 mg/day | 60 mg/day (once daily) | 120 mg/day
Children and Adolescents (7 to 17 years of age) | 30 mg/day | 30 to 60 mg/day (once daily) | 120 mg/day
DPNP (2.3) | 60 mg/day | 60 mg/day (once daily) | 60 mg/day
FM (2.4) | 30 mg/day | 60 mg/day (once daily) | 60 mg/day
Chronic Musculoskeletal Pain (2.5) | 30 mg/day | 60 mg/day (once daily) | 60 mg/day

- Some patients may benefit from starting at 30 mg once daily (2)
- There is no evidence that doses greater than 60 mg/day confers additional benefit, while some adverse reactions were observed to be dose-dependent (2)
- Discontinuing CYMBALTA: Gradually reduce dosage to avoid discontinuation symptoms (2.7, 5.7)
- Hepatic Impairment: Avoid use in patients with chronic liver disease or cirrhosis (5.14)
- Renal Impairment: Avoid use in patients with severe renal impairment, GFR <30 mL/min (5.14)

3 DOSAGE FORMS AND STRENGTHS

20 mg, 30 mg, and 60 mg delayed-release capsules (3)

4 CONTRAINDICATIONS

- Serotonin Syndrome and MAOIs: Do not use MAOIs intended to treat psychiatric disorders with CYMBALTA or within 5 days of stopping treatment with CYMBALTA. Do not use CYMBALTA within 14 days of stopping an MAOI intended to treat psychiatric disorders. In addition, do not start CYMBALTA in a patient who is being treated with linezolid or intravenous methylene blue (4)

5 WARNINGS AND PRECAUTIONS

- Hepatotoxicity: Hepatic failure, sometimes fatal, has been reported in patients treated with CYMBALTA. CYMBALTA should be discontinued in patients who develop jaundice or other evidence of clinically significant liver dysfunction and should not be resumed unless another cause can be established. CYMBALTA should not be prescribed to patients with substantial alcohol use or evidence of chronic liver disease (5.2)
- Orthostatic Hypotension, Falls and Syncope: Cases have been reported with CYMBALTA therapy (5.3)
- Serotonin Syndrome: Serotonin syndrome has been reported with SSRIs and SNRIs, including with CYMBALTA, both when taken alone, but especially when co-administered with other serotonergic agents (including triptans, tricyclic antidepressants, fentanyl, lithium, tramadol, tryptophan, buspirone and St. John's Wort). If such symptoms occur, discontinue CYMBALTA and initiate supportive treatment. If concomitant use of CYMBALTA with other serotonergic drugs is clinically warranted, patients should be made aware of a potential increased risk for serotonin syndrome, particularly during treatment initiation and dose increases (5.4)
- Abnormal Bleeding: CYMBALTA may increase the risk of bleeding events. Patients should be cautioned about the risk of bleeding associated with the concomitant use of CYMBALTA and NSAIDs, aspirin, or other drugs that affect coagulation (5.5, 7.4)
- Severe Skin Reactions: Severe skin reactions, including erythema multiforme and Stevens-Johnson Syndrome (SJS), can occur with CYMBALTA. CYMBALTA should be discontinued at the first appearance of blisters, peeling rash, mucosal erosions, or any other sign of hypersensitivity if no other etiology can be identified. (5.6)
- Discontinuation: May result in symptoms, including dizziness, headache, nausea, diarrhea, paresthesia, irritability, vomiting, insomnia, anxiety, hyperhidrosis, and fatigue (5.7)
- Activation of mania or hypomania has occurred (5.8)
- Angle-Closure Glaucoma: Angle-closure glaucoma has occurred in patients with untreated anatomically narrow angles treated with antidepressants. (5.9)
- Seizures: Prescribe with care in patients with a history of seizure disorder (5.10)
- Blood Pressure: Monitor blood pressure prior to initiating treatment and periodically throughout treatment (5.11)
- Inhibitors of CYP1A2 or Thioridazine: Should not administer with CYMBALTA (5.12)
- Hyponatremia: Cases of hyponatremia have been reported (5.13)
- Glucose Control in Diabetes: In diabetic peripheral neuropathic pain patients, small increases in fasting blood glucose, and HbA1c have been observed (5.14)
- Conditions that Slow Gastric Emptying: Use cautiously in these patients (5.14)
- Urinary Hesitation and Retention (5.15)

6 ADVERSE REACTIONS

- Most common adverse reactions (≥5% and at least twice the incidence of placebo patients): nausea, dry mouth, somnolence, constipation, decreased appetite, and hyperhidrosis (6.3).

To report SUSPECTED ADVERSE REACTIONS, contact Eli Lilly and Company at 1-800-LillyRx (1-800-545-5979) or FDA at 1-800-FDA-1088 or www.fda.gov/medwatch.

7 DRUG INTERACTIONS

- Potent inhibitors of CYP1A2 should be avoided (7.1).
- Potent inhibitors of CYP2D6 may increase CYMBALTA concentrations (7.2).
- CYMBALTA is a moderate inhibitor of CYP2D6 (7.9).

8 USE IN SPECIFIC POPULATIONS

- Pregnancy: Based on animal data may cause fetal harm (8.1)
- Nursing Mothers: Exercise caution when administered to a nursing woman (8.3)

FULL PRESCRIBING INFORMATION

WARNING: SUICIDAL THOUGHTS AND BEHAVIORS

Antidepressants increased the risk of suicidal thoughts and behavior in children, adolescents, and young adults in short-term studies. These studies did not show an increase in the risk of suicidal thoughts and behavior with antidepressant use in patients over age 24; there was a reduction in risk with antidepressant use in patients aged 65 and older [see Warnings and Precautions (5.1)].

In patients of all ages who are started on antidepressant therapy, monitor closely for worsening, and for emergence of suicidal thoughts and behaviors. Advise families and caregivers of the need for close observation and communication with the prescriber [see Warnings and Precautions (5.1)].

1 INDICATIONS AND USAGE

CYMBALTA® is indicated for the treatment of:

- Major Depressive Disorder [see Clinical Studies (14.1)]
- Generalized Anxiety Disorder [see Clinical Studies (14.2)]
- Diabetic Peripheral Neuropathy [see Clinical Studies (14.3)]
- Fibromyalgia [see Clinical Studies (14.4)]
- Chronic Musculoskeletal Pain [see Clinical Studies (14.5)]

2 DOSAGE AND ADMINISTRATION

Swallow CYMBALTA whole. Do not chew or crush. Do not open the capsule and sprinkle its contents on food or mix with liquids. All of these might affect the enteric coating. CYMBALTA can be given without regard to meals. If a dose of CYMBALTA is missed, take the missed dose as soon as it is remembered. If it is almost time for the next dose, skip the missed dose and take the next dose at the regular time. Do not take two doses of CYMBALTA at the same time.

2.1 Dosage for Treatment of Major Depressive Disorder

Administer CYMBALTA at a total dose of 40 mg/day (given as 20 mg twice daily) to 60 mg/day (given either once daily or as 30 mg twice daily). For some patients, it may be desirable to start at 30 mg once daily for 1 week, to allow patients to adjust to the medication before increasing to 60 mg once daily. While a 120 mg/day dose was shown to be effective, there is no evidence that doses greater than 60 mg/day confer any additional benefits. The safety of doses above 120 mg/day has not been adequately evaluated. Periodically reassess to determine the need for maintenance treatment and the appropriate dose for such treatment [see Clinical Studies (14.1)].

2.2 Dosage for Treatment of Generalized Anxiety Disorder

Adults — For most patients, initiate CYMBALTA 60 mg once daily. For some patients, it may be desirable to start at 30 mg once daily for 1 week, to allow patients to adjust to the medication before increasing to 60 mg once daily. While a 120 mg once daily dose was shown to be effective, there is no evidence that doses greater than 60 mg/day confer additional benefit. Nevertheless, if a decision is made to increase the dose beyond 60 mg once daily, increase dose in increments of 30 mg once daily. The safety of doses above 120 mg once daily has not been adequately evaluated. Periodically reassess to determine the continued need for maintenance treatment and the appropriate dose for such treatment [see Clinical Studies (14.2)].

Elderly — Initiate CYMBALTA at a dose of 30 mg once daily for 2 weeks before considering an increase to the target dose of 60 mg. Thereafter, patients may benefit from doses above 60 mg once daily. If a decision is made to increase the dose beyond 60 mg once daily, increase dose in increments of 30 mg once daily. The maximum dose studied was 120 mg per day. Safety of doses above 120 mg once daily has not been adequately evaluated [see Clinical Studies (14.2)].

Children and Adolescents (7 to 17 years of age) — Initiate CYMBALTA at a dose of 30 mg once daily for 2 weeks before considering an increase to 60 mg. The recommended dose range is 30 to 60 mg once daily. Some patients may benefit from doses above 60 mg once daily. If a decision is made to increase the dose beyond 60 mg once daily, increase dose in increments of 30 mg once daily. The maximum dose studied was 120 mg per day. The safety of doses above 120 mg once daily has not been evaluated [see Clinical Studies (14.2)].

2.3 Dosage for Treatment of Diabetic Peripheral Neuropathic Pain

Administer CYMBALTA 60 mg once daily. There is no evidence that doses higher than 60 mg confer additional significant benefit and the higher dose is clearly less well tolerated [see Clinical Studies (14.3)]. For patients for whom tolerability is a concern, a lower starting dose may be considered.

Since diabetes is frequently complicated by renal disease, consider a lower starting dose and gradual increase in dose for patients with renal impairment [see Dosage and Administration (2.6), Use in Specific Populations (8.10), and Clinical Pharmacology (12.3)].

2.4 Dosage for Treatment of Fibromyalgia

Administer CYMBALTA 60 mg once daily. Begin treatment at 30 mg once daily for 1 week, to allow patients to adjust to the medication before increasing to 60 mg once daily. Some patients may respond to the starting dose. There is no evidence that doses greater than 60 mg/day confer additional benefit, even in patients who do not respond to a 60 mg dose, and higher doses are associated with a higher rate of adverse reactions [see Clinical Studies (14.4)].

2.5 Dosage for Treatment of Chronic Musculoskeletal Pain

Administer CYMBALTA 60 mg once daily. Begin treatment at 30 mg for one week, to allow patients to adjust to the medication before increasing to 60 mg once daily. There is no evidence that higher doses confer additional benefit, even in patients who do not respond to a 60 mg dose, and higher doses are associated with a higher rate of adverse reactions [see Clinical Studies (14.5)].

2.6 Dosing in Special Populations

Hepatic Impairment — Avoid use in patients with chronic liver disease or cirrhosis [see Warnings and Precautions (5.14) and Use in Specific Populations (8.9)].

Severe Renal Impairment — Avoid use in patients with severe renal impairment, GFR <30 mL/min [see Warnings and Precautions (5.14) and Use in Specific Populations (8.10)].

2.7 Discontinuing CYMBALTA

Adverse reactions after discontinuation of CYMBALTA, after abrupt or tapered discontinuation, include: dizziness, headache, nausea, diarrhea, paresthesia, irritability, vomiting, insomnia, anxiety, hyperhidrosis, and fatigue. A gradual reduction in dosage rather than abrupt cessation is recommended whenever possible [see Warnings and Precautions (5.7)].

2.8 Switching a Patient to or from a Monoamine Oxidase Inhibitor (MAOI) Intended to Treat Psychiatric Disorders

At least 14 days should elapse between discontinuation of an MAOI intended to treat psychiatric disorders and initiation of therapy with CYMBALTA. Conversely, at least 5 days should be allowed after stopping CYMBALTA before starting an MAOI intended to treat psychiatric disorders [see Contraindications (4)].

2.9 Use of CYMBALTA with Other MAOIs such as Linezolid or Methylene Blue

Do not start CYMBALTA in a patient who is being treated with linezolid or intravenous methylene blue because there is an increased risk of serotonin syndrome. In a patient who requires more urgent treatment of a psychiatric condition, other interventions, including hospitalization, should be considered [see Contraindications (4)].

In some cases, a patient already receiving CYMBALTA therapy may require urgent treatment with linezolid or intravenous methylene blue. If acceptable alternatives to linezolid or intravenous methylene blue treatment are not available and the potential benefits of linezolid or intravenous methylene blue treatment are judged to outweigh the risks of serotonin syndrome in a particular patient, CYMBALTA should be stopped promptly, and linezolid or intravenous methylene blue can be administered. The patient should be monitored for symptoms of serotonin syndrome for 5 days or until 24 hours after the last dose of linezolid or intravenous methylene blue, whichever comes first. Therapy with CYMBALTA may be resumed 24 hours after the last dose of linezolid or intravenous methylene blue [see Warnings and Precautions (5.4)].

The risk of administering methylene blue by non-intravenous routes (such as oral tablets or by local injection) or in intravenous doses much lower than 1 mg/kg with CYMBALTA is unclear. The clinician should, nevertheless, be aware of the possibility of emergent symptoms of serotonin syndrome with such use [see Warnings and Precautions (5.4)].

3 DOSAGE FORMS AND STRENGTHS

CYMBALTA is available as delayed release capsules:

20 mg opaque green capsules imprinted with “Lilly 3235 20mg”

30 mg opaque white and blue capsules imprinted with “Lilly 3240 30mg”

60 mg opaque green and blue capsules imprinted with “Lilly 3270 60mg”

4 CONTRAINDICATIONS

Monoamine Oxidase Inhibitors (MAOIs) — The use of MAOIs intended to treat psychiatric disorders with CYMBALTA or within 5 days of stopping treatment with CYMBALTA is contraindicated because of an increased risk of serotonin syndrome. The use of CYMBALTA within 14 days of stopping an MAOI intended to treat psychiatric disorders is also contraindicated [see Dosage and Administration (2.8) and Warnings and Precautions (5.4)].

Starting CYMBALTA in a patient who is being treated with MAOIs such as linezolid or intravenous methylene blue is also contraindicated because of an increased risk of serotonin syndrome [see Dosage and Administration (2.9) and Warnings and Precautions (5.4)].

5 WARNINGS AND PRECAUTIONS

5.1 Suicidal Thoughts and Behaviors in Children, Adolescents, and Young Adults

Patients with major depressive disorder (MDD), both adult and pediatric, may experience worsening of their depression and/or the emergence of suicidal ideation and behavior (suicidality) or unusual changes in behavior, whether or not they are taking antidepressant medications, and this risk may persist until significant remission occurs. Suicide is a known risk of depression and certain other psychiatric disorders, and these disorders themselves are the strongest predictors of suicide. There has been a long-standing concern, however, that antidepressants may have a role in inducing worsening of depression and the emergence of suicidality in certain patients during the early phases of treatment.

Pooled analyses of short-term placebo-controlled trials of antidepressant drugs (SSRIs and others) showed that these drugs increase the risk of suicidal thinking and behavior (suicidality) in children, adolescents, and young adults (ages 18-24) with major depressive disorder (MDD) and other psychiatric disorders. Short-term studies did not show an increase in the risk of suicidality with antidepressants compared to placebo in adults beyond age 24; there was a reduction with antidepressants compared to placebo in adults aged 65 and older.

The pooled analyses of placebo-controlled trials in children and adolescents with MDD, obsessive compulsive disorder (OCD), or other psychiatric disorders included a total of 24 short-term trials of 9 antidepressant drugs in over 4400 patients. The pooled analyses of placebo-controlled trials in adults with MDD or other psychiatric disorders included a total of 295 short-term trials (median duration of 2 months) of 11 antidepressant drugs in over 77,000 patients. There was considerable variation in risk of suicidality among drugs, but a tendency toward an increase in the younger patients for almost all drugs studied. There were differences in absolute risk of suicidality across the different indications, with the highest incidence in MDD. The risk of differences (drug vs placebo), however, were relatively stable within age strata and across indications. These risk differences (drug-placebo difference in the number of cases of suicidality per 1000 patients treated) are provided in Table 1.

Table 1
Age Range | Drug-Placebo Difference in Number of Cases of Suicidality per 1000 Patients Treated
 | Increases Compared to Placebo
<18 | 14 additional cases
18-24 | 5 additional cases
 | Decreases Compared to Placebo
25-64 | 1 fewer case
≥65 | 6 fewer cases

No suicides occurred in any of the pediatric trials. There were suicides in the adult trials, but the number was not sufficient to reach any conclusion about drug effect on suicide.

It is unknown whether the suicidality risk extends to longer-term use, i.e., beyond several months. However, there is substantial evidence from placebo-controlled maintenance trials in adults with depression that the use of antidepressants can delay the recurrence of depression.

All patients being treated with antidepressants for any indication should be monitored appropriately and observed closely for clinical worsening, suicidality, and unusual changes in behavior, especially during the initial few months of a course of drug therapy, or at times of dose changes, either increases or decreases.

The following symptoms, anxiety, agitation, panic attacks, insomnia, irritability, hostility, aggressiveness, impulsivity, akathisia (psychomotor restlessness), hypomania, and mania, have been reported in adult and pediatric patients being treated with antidepressants for major depressive disorder as well as for other indications, both psychiatric and nonpsychiatric. Although a causal link between the emergence of such symptoms and either the worsening of depression and/or the emergence of suicidal impulses has not been established, there is concern that such symptoms may represent precursors to emerging suicidality.

Consideration should be given to changing the therapeutic regimen, including possibly discontinuing the medication, in patients whose depression is persistently worse, or who are experiencing emergent suicidality or symptoms that might be precursors to worsening depression or suicidality, especially if these symptoms are severe, abrupt in onset, or were not part of the patient's presenting symptoms.

If the decision has been made to discontinue treatment, medication should be tapered, as rapidly as is feasible, but with recognition that discontinuation can be associated with certain symptoms [see Dosage and Administration (2.7) and Warnings and Precautions (5.7) for descriptions of the risks of discontinuation of CYMBALTA].

Families and caregivers of patients being treated with antidepressants for major depressive disorder or other indications, both psychiatric and nonpsychiatric, should be alerted about the need to monitor patients for the emergence of agitation, irritability, unusual changes in behavior, and the other symptoms described above, as well as the emergence of suicidality, and to report such symptoms immediately to health care providers. Such monitoring should include daily observation by families and caregivers. Prescriptions for CYMBALTA should be written for the smallest quantity of capsules consistent with good patient management, in order to reduce the risk of overdose.

Screening Patients for Bipolar Disorder — A major depressive episode may be the initial presentation of bipolar disorder. It is generally believed (though not established in controlled trials) that treating such an episode with an antidepressant alone may increase the likelihood of precipitation of a mixed/manic episode in patients at risk for bipolar disorder. Whether any of the symptoms described above represent such a conversion is unknown. However, prior to initiating treatment with an antidepressant, patients with depressive symptoms should be adequately screened to determine if they are at risk for bipolar disorder; such screening should include a detailed psychiatric history, including a family history of suicide, bipolar disorder, and depression. It should be noted that CYMBALTA is not approved for use in treating bipolar depression.

5.2 Hepatotoxicity

There have been reports of hepatic failure, sometimes fatal, in patients treated with CYMBALTA. These cases have presented as hepatitis with abdominal pain, hepatomegaly, and elevation of transaminase levels to more than twenty times the upper limit of normal with or without jaundice, reflecting a mixed or hepatocellular pattern of liver injury. CYMBALTA should be discontinued in patients who develop jaundice or other evidence of clinically significant liver dysfunction and should not be resumed unless another cause can be established.

Cases of cholestatic jaundice with minimal elevation of transaminase levels have also been reported. Other postmarketing reports indicate that elevated transaminases, bilirubin, and alkaline phosphatase have occurred in patients with chronic liver disease or cirrhosis.

CYMBALTA increased the risk of elevation of serum transaminase levels in development program clinical trials. Liver transaminase elevations resulted in the discontinuation of 0.3% (92/34,756) of CYMBALTA-treated patients. In most patients, the median time to detection of the transaminase elevation was about two months. In adult placebo-controlled trials in any indication, for patients with normal and abnormal baseline ALT values, elevation of ALT >3 times the upper limit of normal occurred in 1.25% (144/11,496) of CYMBALTA-treated patients compared to 0.45% (39/8716) of placebo-treated patients. In adult placebo-controlled studies using a fixed dose design, there was evidence of a dose response relationship for ALT and AST elevation of >3 times the upper limit of normal and >5 times the upper limit of normal, respectively.

Because it is possible that CYMBALTA and alcohol may interact to cause liver injury or that CYMBALTA may aggravate pre-existing liver disease, CYMBALTA should not be prescribed to patients with substantial alcohol use or evidence of chronic liver disease.

5.3 Orthostatic Hypotension, Falls and Syncope

Orthostatic hypotension, falls and syncope have been reported with therapeutic doses of CYMBALTA. Syncope and orthostatic hypotension tend to occur within the first week of therapy but can occur at any time during CYMBALTA treatment, particularly after dose increases. The risk of falling appears to be related to the degree of orthostatic decrease in blood pressure as well as other factors that may increase the underlying risk of falls.

In an analysis of patients from all placebo-controlled trials, patients treated with CYMBALTA reported a higher rate of falls compared to patients treated with placebo. Risk appears to be related to the presence of orthostatic decrease in blood pressure. The risk of blood pressure decreases may be greater in patients taking concomitant medications that induce orthostatic hypotension (such as antihypertensives) or are potent CYP1A2 inhibitors [see Warnings and Precautions (5.12) and Drug Interactions (7.1)] and in patients taking CYMBALTA at doses above 60 mg daily. Consideration should be given to dose reduction or discontinuation of CYMBALTA in patients who experience symptomatic orthostatic hypotension, falls and/or syncope during CYMBALTA therapy.

Risk of falling also appeared to be proportional to a patient's underlying risk for falls and appeared to increase steadily with age. As elderly patients tend to have a higher underlying risk for falls due to a higher prevalence of risk factors such as use of multiple medications, medical comorbidities and gait disturbances, the impact of increasing age by itself is unclear. Falls with serious consequences including bone fractures and hospitalizations have been reported [see Adverse Reactions (6.10) and Patient Counseling Information (17)].

5.4 Serotonin Syndrome

The development of a potentially life-threatening serotonin syndrome has been reported with SNRIs and SSRIs, including CYMBALTA, alone but particularly with concomitant use of other serotonergic drugs (including triptans, tricyclic antidepressants, fentanyl, lithium, tramadol, tryptophan, buspirone, and St. John's Wort) and with drugs that impair metabolism of serotonin (in particular, MAOIs, both those intended to treat psychiatric disorders and also others, such as linezolid and intravenous methylene blue).

Serotonin syndrome symptoms may include mental status changes (e.g., agitation, hallucinations, delirium, and coma), autonomic instability (e.g., tachycardia, labile blood pressure, dizziness, diaphoresis, flushing, hyperthermia), neuromuscular symptoms (e.g., tremor, rigidity, myoclonus, hyperreflexia, incoordination), seizures, and/or gastrointestinal symptoms (e.g., nausea, vomiting, diarrhea). Patients should be monitored for the emergence of serotonin syndrome.

The concomitant use of CYMBALTA with MAOIs intended to treat psychiatric disorders is contraindicated. CYMBALTA should also not be started in a patient who is being treated with MAOIs such as linezolid or intravenous methylene blue. All reports with methylene blue that provided information on the route of administration involved intravenous administration in the dose range of 1 mg/kg to 8 mg/kg. No reports involved the administration of methylene blue by other routes (such as oral tablets or local tissue injection) or at lower doses. There may be circumstances when it is necessary to initiate treatment with an MAOI such as linezolid or intravenous methylene blue in a patient taking CYMBALTA. CYMBALTA should be discontinued before initiating treatment with the MAOI [see Dosage and Administration (2.8, 2.9), and Contraindications (4)].

If concomitant use of CYMBALTA with other serotonergic drugs including triptans, tricyclic antidepressants, fentanyl, lithium, tramadol, buspirone, tryptophan and St. John's Wort is clinically warranted, patients should be made aware of a potential increased risk for serotonin syndrome, particularly during treatment initiation and dose increases. Treatment with CYMBALTA and any concomitant serotonergic agents, should be discontinued immediately if the above events occur and supportive symptomatic treatment should be initiated.

5.5 Abnormal Bleeding

SSRIs and SNRIs, including CYMBALTA, may increase the risk of bleeding events. Concomitant use of aspirin, nonsteroidal anti-inflammatory drugs, warfarin, and other anti-coagulants may add to this risk. Case reports and epidemiological studies (case-control and cohort design) have demonstrated an association between use of drugs that interfere with serotonin reuptake and the occurrence of gastrointestinal bleeding. Bleeding events related to SSRIs and SNRIs use have ranged from ecchymoses, hematomas, epistaxis, and petechiae to life-threatening hemorrhages.

Patients should be cautioned about the risk of bleeding associated with the concomitant use of CYMBALTA and NSAIDs, aspirin, or other drugs that affect coagulation.

5.6 Severe Skin Reactions

Severe skin reactions, including erythema multiforme and Stevens-Johnson Syndrome (SJS), can occur with CYMBALTA. The reporting rate of SJS associated with CYMBALTA use exceeds the general population background incidence rate for this serious skin reaction (1 to 2 cases per million person years). The reporting rate is generally accepted to be an underestimate due to underreporting.

CYMBALTA should be discontinued at the first appearance of blisters, peeling rash, mucosal erosions, or any other sign of hypersensitivity if no other etiology can be identified.

5.7 Discontinuation of Treatment with CYMBALTA

Discontinuation symptoms have been systematically evaluated in patients taking CYMBALTA. Following abrupt or tapered discontinuation in adult placebo-controlled clinical trials, the following symptoms occurred at 1% or greater and at a significantly higher rate in CYMBALTA-treated patients compared to those discontinuing from placebo: dizziness, headache, nausea, diarrhea, paresthesia, irritability, vomiting, insomnia, anxiety, hyperhidrosis, and fatigue.

During marketing of other SSRIs and SNRIs (serotonin and norepinephrine reuptake inhibitors), there have been spontaneous reports of adverse events occurring upon discontinuation of these drugs, particularly when abrupt, including the following: dysphoric mood, irritability, agitation, dizziness, sensory disturbances (e.g., paresthesias such as electric shock sensations), anxiety, confusion, headache, lethargy, emotional lability, insomnia, hypomania, tinnitus, and seizures. Although these events are generally self-limiting, some have been reported to be severe.

Patients should be monitored for these symptoms when discontinuing treatment with CYMBALTA. A gradual reduction in the dose rather than abrupt cessation is recommended whenever possible. If intolerable symptoms occur following a decrease in the dose or upon discontinuation of treatment, then resuming the previously prescribed dose may be considered. Subsequently, the physician may continue decreasing the dose but at a more gradual rate [see Dosage and Administration (2.7)].

5.8 Activation of Mania/Hypomania

In adult placebo-controlled trials in patients with major depressive disorder, activation of mania or hypomania was reported in 0.1% (4/3779) of CYMBALTA-treated patients and 0.04% (1/2536) of placebo-treated patients. No activation of mania or hypomania was reported in DPNP, GAD, fibromyalgia, or chronic musculoskeletal pain placebo-controlled trials. Activation of mania or hypomania has been reported in a small proportion of patients with mood disorders who were treated with other marketed drugs effective in the treatment of major depressive disorder. As with these other agents, CYMBALTA should be used cautiously in patients with a history of mania.

5.9 Angle-Closure Glaucoma

The pupillary dilation that occurs following use of many antidepressant drugs including CYMBALTA may trigger an angle closure attack in a patient with anatomically narrow angles who does not have a patent iridectomy.

5.10 Seizures

CYMBALTA has not been systematically evaluated in patients with a seizure disorder, and such patients were excluded from clinical studies. In adult placebo-controlled clinical trials, seizures/convulsions occurred in 0.02% (3/12,722) of patients treated with CYMBALTA and 0.01% (1/9513) of patients treated with placebo. CYMBALTA should be prescribed with care in patients with a history of a seizure disorder.

5.11 Effect on Blood Pressure

In adult placebo-controlled clinical trials across indications from baseline to endpoint, CYMBALTA treatment was associated with mean increases of 0.5 mm Hg in systolic blood pressure and 0.8 mm Hg in diastolic blood pressure compared to mean decreases of 0.6 mm Hg systolic and 0.3 mm Hg diastolic in placebo-treated patients. There was no significant difference in the frequency of sustained (3 consecutive visits) elevated blood pressure. In a clinical pharmacology study designed to evaluate the effects of CYMBALTA on various parameters, including blood pressure at supratherapeutic doses with an accelerated dose titration, there was evidence of increases in supine blood pressure at doses up to 200 mg twice daily. At the highest 200 mg twice daily dose, the increase in mean pulse rate was 5.0 to 6.8 beats and increases in mean blood pressure were 4.7 to 6.8 mm Hg (systolic) and 4.5 to 7 mm Hg (diastolic) up to 12 hours after dosing.

Blood pressure should be measured prior to initiating treatment and periodically measured throughout treatment [see Adverse Reactions (6.7)].

5.12 Clinically Important Drug Interactions

Both CYP1A2 and CYP2D6 are responsible for CYMBALTA metabolism.

Potential for Other Drugs to Affect CYMBALTA

CYP1A2 Inhibitors — Co-administration of CYMBALTA with potent CYP1A2 inhibitors should be avoided [see Drug Interactions (7.1)].

CYP2D6 Inhibitors — Because CYP2D6 is involved in CYMBALTA metabolism, concomitant use of CYMBALTA with potent inhibitors of CYP2D6 would be expected to, and does, result in higher concentrations (on average of 60%) of CYMBALTA [see Drug Interactions (7.2)].

Potential for CYMBALTA to Affect Other Drugs

Drugs Metabolized by CYP2D6 — Co-administration of CYMBALTA with drugs that are extensively metabolized by CYP2D6 and that have a narrow therapeutic index, including certain antidepressants (tricyclic antidepressants [TCAs], such as nortriptyline, amitriptyline, and imipramine), phenothiazines and Type 1C antiarrhythmics (e.g., propafenone, flecainide), should be approached with caution. Plasma TCA concentrations may need to be monitored and the dose of the TCA may need to be reduced if a TCA is co-administered with CYMBALTA. Because of the risk of serious ventricular arrhythmias and sudden death potentially associated with elevated plasma levels of thioridazine, CYMBALTA and thioridazine should not be co-administered [see Drug Interactions (7.9)].

Other Clinically Important Drug Interactions

Alcohol — Use of CYMBALTA concomitantly with heavy alcohol intake may be associated with severe liver injury. For this reason, CYMBALTA should not be prescribed for patients with substantial alcohol use [see Warnings and Precautions (5.2) and Drug Interactions (7.15)].

CNS Acting Drugs — Given the primary CNS effects of CYMBALTA, it should be used with caution when it is taken in combination with or substituted for other centrally acting drugs, including those with a similar mechanism of action [see Warnings and Precautions (5.12) and Drug Interactions (7.16)].

5.13 Hyponatremia

Hyponatremia may occur as a result of treatment with SSRIs and SNRIs, including CYMBALTA. In many cases, this hyponatremia appears to be the result of the syndrome of inappropriate antidiuretic hormone secretion (SIADH). Cases with serum sodium lower than 110 mmol/L have been reported and appeared to be reversible when CYMBALTA was discontinued. Elderly patients may be at greater risk of developing hyponatremia with SSRIs and SNRIs. Also, patients taking diuretics or who are otherwise volume depleted may be at greater risk [see Use in Specific Populations (8.5)]. Discontinuation of CYMBALTA should be considered in patients with symptomatic hyponatremia and appropriate medical intervention should be instituted.

Signs and symptoms of hyponatremia include headache, difficulty concentrating, memory impairment, confusion, weakness, and unsteadiness, which may lead to falls. More severe and/or acute cases have been associated with hallucination, syncope, seizure, coma, respiratory arrest, and death.

5.14 Use in Patients with Concomitant Illness

Clinical experience with CYMBALTA in patients with concomitant systemic illnesses is limited. There is no information on the effect that alterations in gastric motility may have on the stability of CYMBALTA's enteric coating. In extremely acidic conditions, CYMBALTA, unprotected by the enteric coating, may undergo hydrolysis to form naphthol. Caution is advised in using CYMBALTA in patients with conditions that may slow gastric emptying (e.g., some diabetics).

CYMBALTA has not been systematically evaluated in patients with a recent history of myocardial infarction or unstable coronary artery disease. Patients with these diagnoses were generally excluded from clinical studies during the product's premarketing testing.

Hepatic Impairment — Avoid use in patients with chronic liver disease or cirrhosis [see Dosage and Administration (2.6), Warnings and Precautions (5.2), and Use in Specific Populations (8.9)].

Severe Renal Impairment — Avoid use in patients with severe renal impairment, GFR <30 mL/min. Increased plasma concentration of CYMBALTA, and especially of its metabolites, occur in patients with end-stage renal disease (requiring dialysis) [see Dosage and Administration (2.6) and Use in Specific Populations (8.10)].

Glycemic Control in Patients with Diabetes — As observed in DPNP trials, CYMBALTA treatment worsens glycemic control in some patients with diabetes. In three clinical trials of CYMBALTA for the management of neuropathic pain associated with diabetic peripheral neuropathy, the mean duration of diabetes was approximately 12 years, the mean baseline fasting blood glucose was 176 mg/dL, and the mean baseline hemoglobin A1c (HbA1c) was 7.8%. In the 12-week acute treatment phase of these studies, CYMBALTA was associated with a small increase in mean fasting blood glucose as compared to placebo. In the extension phase of these studies, which lasted up to 52 weeks, mean fasting blood glucose increased by 12 mg/dL in the CYMBALTA group and decreased by 11.5 mg/dL in the routine care group. HbA1c increased by 0.5% in the CYMBALTA and by 0.2% in the routine care groups.

5.15 Urinary Hesitation and Retention

CYMBALTA is in a class of drugs known to affect urethral resistance. If symptoms of urinary hesitation develop during treatment with CYMBALTA, consideration should be given to the possibility that they might be drug-related.

In post marketing experience, cases of urinary retention have been observed. In some instances of urinary retention associated with CYMBALTA use, hospitalization and/or catheterization has been needed.

5.16 Laboratory Tests

No specific laboratory tests are recommended.

6 ADVERSE REACTIONS

The following serious adverse reactions are described below and elsewhere in the labeling:

- Suicidal Thoughts and Behaviors in Children, Adolescents and Young Adults [see Boxed Warning and Warnings and Precautions (5.1)]
- Hepatotoxicity [see Warnings and Precautions (5.2)]
- Orthostatic Hypotension, Falls and Syncope [see Warnings and Precautions (5.3)]
- Serotonin Syndrome [see Warnings and Precautions (5.4)]
- Abnormal Bleeding [see Warnings and Precautions (5.5)]
- Severe Skin Reactions [see Warnings and Precautions (5.6)]
- Discontinuation of Treatment with CYMBALTA [see Warnings and Precautions (5.7)]
- Activation of Mania/Hypomania [see Warnings and Precautions (5.8)]
- Angle-Closure Glaucoma [see Warnings and Precautions (5.9)]
- Seizures [see Warnings and Precautions (5.10)]
- Effect on Blood Pressure [see Warnings and Precautions (5.11)]
- Clinically Important Drug Interactions [see Warnings and Precautions (5.12)]
- Hyponatremia [see Warnings and Precautions (5.13)]
- Urinary Hesitation and Retention [see Warnings and Precautions (5.15)]

6.1 Clinical Trial Data Sources

Because clinical trials are conducted under widely varying conditions, adverse reaction rates observed in the clinical trials of a drug cannot be directly compared to rates in the clinical trials of another drug and may not reflect the rates observed in practice.

The stated frequencies of adverse reactions represent the proportion of individuals who experienced, at least once, a treatment-emergent adverse reaction of the type listed. A reaction was considered treatment-emergent if it occurred for the first time or worsened while receiving therapy following baseline evaluation. Reactions reported during the studies were not necessarily caused by the therapy, and the frequencies do not reflect investigator impression (assessment) of causality.

Adults — The data described below reflect exposure to CYMBALTA in placebo-controlled trials for MDD (N=3779), GAD (N=1018), OA (N=503), CLBP (N=600), DPNP (N=906), and FM (N=1294). The population studied was 17 to 89 years of age; 65.7%, 60.8%, 60.6%, 42.9%, and 94.4% female; and 81.8%, 72.6%, 85.3%, 74.0%, and 85.7% Caucasian for MDD, GAD, OA and CLBP, DPNP, and FM, respectively. Most patients received doses of a total of 60 to 120 mg per day [see Clinical Studies (14)].The data below do not include results of the trial examining the efficacy of CYMBALTA in patients ≥ 65 years old for the treatment of generalized anxiety disorder; however, the adverse reactions observed in this geriatric sample were generally similar to adverse reactions in the overall adult population.

Children and Adolescents — The data described below reflect exposure to CYMBALTA in pediatric, 10-week, placebo-controlled trials for MDD (N=341) and GAD (N=135). The population studied (N=476) was 7 to 17 years of age with 42.4% children age 7 to 11 years of age, 50.6% female, and 68.6% white. Patients received 30-120 mg per day during placebo-controlled acute treatment studies. Additional data come from the overall total of 822 pediatric patients (age 7 to 17 years of age) with 41.7% children age 7 to 11 years of age and 51.8% female exposed to CYMBALTA in MDD and GAD clinical trials up to 36-weeks in length, in which most patients received 30-120 mg per day.

6.2 Adverse Reactions Reported as Reasons for Discontinuation of Treatment in Adult Placebo-Controlled Trials

Major Depressive Disorder — Approximately 8.4% (319/3779) of the patients who received CYMBALTA in placebo-controlled trials for MDD discontinued treatment due to an adverse reaction, compared with 4.6% (117/2536) of the patients receiving placebo. Nausea (CYMBALTA 1.1%, placebo 0.4%) was the only common adverse reaction reported as a reason for discontinuation and considered to be drug-related (i.e., discontinuation occurring in at least 1% of the CYMBALTA-treated patients and at a rate of at least twice that of placebo).

Generalized Anxiety Disorder — Approximately 13.7% (139/1018) of the patients who received CYMBALTA in placebo-controlled trials for GAD discontinued treatment due to an adverse reaction, compared with 5.0% (38/767) for placebo. Common adverse reactions reported as a reason for discontinuation and considered to be drug-related (as defined above) included nausea (CYMBALTA 3.3%, placebo 0.4%), and dizziness (CYMBALTA 1.3%, placebo 0.4%).

Diabetic Peripheral Neuropathic Pain — Approximately 12.9% (117/906) of the patients who received CYMBALTA in placebo-controlled trials for DPNP discontinued treatment due to an adverse reaction, compared with 5.1% (23/448) for placebo. Common adverse reactions reported as a reason for discontinuation and considered to be drug-related (as defined above) included nausea (CYMBALTA 3.5%, placebo 0.7%), dizziness (CYMBALTA 1.2%, placebo 0.4%), and somnolence (CYMBALTA 1.1%, placebo 0.0%).

Fibromyalgia — Approximately 17.5% (227/1294) of the patients who received CYMBALTA in 3 to 6 month placebo-controlled trials for FM discontinued treatment due to an adverse reaction, compared with 10.1% (96/955) for placebo. Common adverse reactions reported as a reason for discontinuation and considered to be drug-related (as defined above) included nausea (CYMBALTA 2.0%, placebo 0.5%), headache (CYMBALTA 1.2%, placebo 0.3%), somnolence (CYMBALTA 1.1%, placebo 0.0%), and fatigue (CYMBALTA 1.1%, placebo 0.1%).

Chronic Pain due to Osteoarthritis — Approximately 15.7% (79/503) of the patients who received CYMBALTA in 13-week, placebo-controlled trials for chronic pain due to OA discontinued treatment due to an adverse reaction, compared with 7.3% (37/508) for placebo. Common adverse reactions reported as a reason for discontinuation and considered to be drug-related (as defined above) included nausea (CYMBALTA 2.2%, placebo 1.0%).

Chronic Low Back Pain — Approximately 16.5% (99/600) of the patients who received CYMBALTA in 13-week, placebo-controlled trials for CLBP discontinued treatment due to an adverse reaction, compared with 6.3% (28/441) for placebo. Common adverse reactions reported as a reason for discontinuation and considered to be drug-related (as defined above) included nausea (CYMBALTA 3.0%, placebo 0.7%), and somnolence (CYMBALTA 1.0%, placebo 0.0%).

6.3 Most Common Adult Adverse Reactions

Pooled Trials for all Approved Indications — The most commonly observed adverse reactions in CYMBALTA-treated patients (incidence of at least 5% and at least twice the incidence in placebo patients) were nausea, dry mouth, somnolence, constipation, decreased appetite, and hyperhidrosis.

Diabetic Peripheral Neuropathic Pain — The most commonly observed adverse reactions in CYMBALTA-treated patients (as defined above) were nausea, somnolence, decreased appetite, constipation, hyperhidrosis, and dry mouth.

Fibromyalgia — The most commonly observed adverse reactions in CYMBALTA-treated patients (as defined above) were nausea, dry mouth, constipation, somnolence, decreased appetite, hyperhidrosis, and agitation.

Chronic Pain due to Osteoarthritis — The most commonly observed adverse reactions in CYMBALTA-treated patients (as defined above) were nausea, fatigue, constipation, dry mouth, insomnia, somnolence, and dizziness.

Chronic Low Back Pain — The most commonly observed adverse reactions in CYMBALTA-treated patients (as defined above) were nausea, dry mouth, insomnia, somnolence, constipation, dizziness, and fatigue.

6.4 Adverse Reactions Occurring at an Incidence of 5% or More Among CYMBALTA-Treated Patients in Adult Placebo-Controlled Trials

Table 2 gives the incidence of treatment-emergent adverse reactions in placebo-controlled trials for approved indications that occurred in 5% or more of patients treated with CYMBALTA and with an incidence greater than placebo.

Table 2: Treatment-Emergent Adverse Reactions: Incidence of 5% or More and Greater than Placebo in Placebo-Controlled Trials of Approved Indicationsa
 | Percentage of Patients Reporting Reaction
Adverse Reaction | CYMBALTA (N=8100) | Placebo (N=5655)
Nauseac | 23 | 8
Headache | 14 | 12
Dry mouth | 13 | 5
Somnolencee | 10 | 3
Fatigueb,c | 9 | 5
Insomniad | 9 | 5
Constipationc | 9 | 4
Dizzinessc | 9 | 5
Diarrhea | 9 | 6
Decreased appetitec | 7 | 2
Hyperhidrosisc | 6 | 1
Abdominal painf | 5 | 4
a The inclusion of an event in the table is determined based on the percentages before rounding; however, the percentages displayed in the table are rounded to the nearest integer.
b Also includes asthenia.
c Events for which there was a significant dose-dependent relationship in fixed-dose studies, excluding three MDD studies which did not have a placebo lead-in period or dose titration.
d Also includes initial insomnia, middle insomnia, and early morning awakening.
e Also includes hypersomnia and sedation.
f Also includes abdominal discomfort, abdominal pain lower, abdominal pain upper, abdominal tenderness, and gastrointestinal pain.

6.5 Adverse Reactions Occurring at an Incidence of 2% or More Among CYMBALTA-Treated Patients in Adult Placebo-Controlled Trials

Pooled MDD and GAD Trials — Table 3 gives the incidence of treatment-emergent adverse reactions in MDD and GAD placebo-controlled trials for approved indications that occurred in 2% or more of patients treated with CYMBALTA and with an incidence greater than placebo.

Table 3: Treatment-Emergent Adverse Reactions: Incidence of 2% or More and Greater than Placebo in MDD and GAD Placebo-Controlled Trialsa,b
 | Percentage of Patients Reporting Reaction
System Organ Class / Adverse Reaction | CYMBALTA (N=4797) | Placebo (N=3303)
Cardiac Disorders
Palpitations | 2 | 1
Eye Disorders
Vision blurred | 3 | 1
Gastrointestinal Disorders
Nauseac | 23 | 8
Dry mouth | 14 | 6
Constipationc | 9 | 4
Diarrhea | 9 | 6
Abdominal paind | 5 | 4
Vomiting | 4 | 2
General Disorders and Administration Site Conditions
Fatiguee | 9 | 5
Metabolism and Nutrition Disorders
Decreased appetitec | 6 | 2
Nervous System Disorders
Headache | 14 | 14
Dizzinessc | 9 | 5
Somnolencef | 9 | 3
Tremor | 3 | 1
Psychiatric Disorders
Insomniag | 9 | 5
Agitationh | 4 | 2
Anxiety | 3 | 2
Reproductive System and Breast Disorders
Erectile dysfunction | 4 | 1
Ejaculation delayedc | 2 | 1
Libido decreasedi | 3 | 1
Orgasm abnormalj | 2 | <1
Respiratory, Thoracic, and Mediastinal Disorders
Yawning | 2 | <1
Skin and Subcutaneous Tissue Disorders
Hyperhidrosis | 6 | 2
a The inclusion of an event in the table is determined based on the percentages before rounding; however, the percentages displayed in the table are rounded to the nearest integer.
b For GAD, there were no adverse events that were significantly different between treatments in adults ≥65 years that were also not significant in the adults <65 years.
c Events for which there was a significant dose-dependent relationship in fixed-dose studies, excluding three MDD studies which did not have a placebo lead-in period or dose titration.
d Also includes abdominal pain upper, abdominal pain lower, abdominal tenderness, abdominal discomfort, and gastrointestinal pain
e Also includes asthenia
f Also includes hypersomnia and sedation
g Also includes initial insomnia, middle insomnia, and early morning awakening
h Also includes feeling jittery, nervousness, restlessness, tension and psychomotor hyperactivity
i Also includes loss of libido
j Also includes anorgasmia

DPNP, FM, OA, and CLBP — Table 4 gives the incidence of treatment-emergent adverse events that occurred in 2% or more of patients treated with CYMBALTA (determined prior to rounding) in the premarketing acute phase of DPNP, FM, OA, and CLBP placebo-controlled trials and with an incidence greater than placebo.

Table 4: Treatment-Emergent Adverse Reactions: Incidence of 2% or More and Greater than Placebo in DPNP, FM, OA, and CLBP Placebo-Controlled Trialsa
 | Percentage of Patients Reporting Reaction
System Organ Class / Adverse Reaction | CYMBALTA (N=3303) | Placebo (N=2352)
Gastrointestinal Disorders
Nausea | 23 | 7
Dry Mouthb | 11 | 3
Constipationb | 10 | 3
Diarrhea | 9 | 5
Abdominal Painc | 5 | 4
Vomiting | 3 | 2
Dyspepsia | 2 | 1
General Disorders and Administration Site Conditions
Fatigued | 11 | 5
Infections and Infestations
Nasopharyngitis | 4 | 4
Upper Respiratory Tract Infection | 3 | 3
Influenza | 2 | 2
Metabolism and Nutrition Disorders
Decreased Appetiteb | 8 | 1
Musculoskeletal and Connective Tissue
Musculoskeletal Paine | 3 | 3
Muscle Spasms | 2 | 2
Nervous System Disorders
Headache | 13 | 8
Somnolenceb,f | 11 | 3
Dizziness | 9 | 5
Paraesthesiag | 2 | 2
Tremorb | 2 | <1
Psychiatric Disorders
Insomniab,h | 10 | 5
Agitationi | 3 | 1
Reproductive System and Breast Disorders
Erectile Dysfunctionb | 4 | <1
Ejaculation Disorderj | 2 | <1
Respiratory, Thoracic, and Mediastinal Disorders
Cough | 2 | 2
Skin and Subcutaneous Tissue Disorders
Hyperhidrosis | 6 | 1
Vascular Disorders
Flushingk | 3 | 1
Blood pressure increasedl | 2 | 1
a The inclusion of an event in the table is determined based on the percentages before rounding; however, the percentages displayed in the table are rounded to the nearest integer.
b Incidence of 120 mg/day is significantly greater than the incidence for 60 mg/day.
c Also includes abdominal discomfort, abdominal pain lower, abdominal pain upper, abdominal tenderness and gastrointestinal pain
d Also includes asthenia
e Also includes myalgia and neck pain
f Also includes hypersomnia and sedation
g Also includes hypoaesthesia, hypoaesthesia facial, genital hypoaesthesia and paraesthesia oral
h Also includes initial insomnia, middle insomnia, and early morning awakening.
i Also includes feeling jittery, nervousness, restlessness, tension and psychomotor hyperactivity
j Also includes ejaculation failure
k Also includes hot flush
l Also includes blood pressure diastolic increased, blood pressure systolic increased, diastolic hypertension, essential hypertension, hypertension, hypertensive crisis, labile hypertension, orthostatic hypertension, secondary hypertension, and systolic hypertension

6.6 Effects on Male and Female Sexual Function in Adults

Changes in sexual desire, sexual performance and sexual satisfaction often occur as manifestations of psychiatric disorders or diabetes, but they may also be a consequence of pharmacologic treatment. Because adverse sexual reactions are presumed to be voluntarily underreported, the Arizona Sexual Experience Scale (ASEX), a validated measure designed to identify sexual side effects, was used prospectively in 4 MDD placebo-controlled trials. In these trials, as shown in Table 5 below, patients treated with CYMBALTA experienced significantly more sexual dysfunction, as measured by the total score on the ASEX, than did patients treated with placebo. Gender analysis showed that this difference occurred only in males. Males treated with CYMBALTA experienced more difficulty with ability to reach orgasm (ASEX Item 4) than males treated with placebo. Females did not experience more sexual dysfunction on CYMBALTA than on placebo as measured by ASEX total score. Negative numbers signify an improvement from a baseline level of dysfunction, which is commonly seen in depressed patients. Physicians should routinely inquire about possible sexual side effects.

Table 5: Mean Change in ASEX Scores by Gender in MDD Placebo-Controlled Trials
 | Male Patientsa |  | Female Patientsa
 | CYMBALTA (n=175) | Placebo (n=83) | CYMBALTA (n=241) | Placebo (n=126)
ASEX Total (Items 1-5) | 0.56b | -1.07 | -1.15 | -1.07
Item 1 — Sex drive | -0.07 | -0.12 | -0.32 | -0.24
Item 2 — Arousal | 0.01 | -0.26 | -0.21 | -0.18
Item 3 — Ability to achieve erection (men); Lubrication (women) | 0.03 | -0.25 | -0.17 | -0.18
Item 4 — Ease of reaching orgasm | 0.40c | -0.24 | -0.09 | -0.13
Item 5 — Orgasm satisfaction | 0.09 | -0.13 | -0.11 | -0.17
a n=Number of patients with non-missing change score for ASEX total
b p=0.013 versus placebo
c p<0.001 versus placebo

6.7 Vital Sign Changes in Adults

In placebo-controlled clinical trials across approved indications for change from baseline to endpoint, CYMBALTA treatment was associated with mean increases of 0.23 mm Hg in systolic blood pressure and 0.73 mm Hg in diastolic blood pressure compared to mean decreases of 1.09 mm Hg systolic and 0.55 mm Hg diastolic in placebo-treated patients. There was no significant difference in the frequency of sustained (3 consecutive visits) elevated blood pressure [see Warnings and Precautions (5.3, 5.11)].

CYMBALTA treatment, for up to 26 weeks in placebo-controlled trials across approved indications, typically caused a small increase in heart rate for change from baseline to endpoint compared to placebo of up to 1.37 beats per minute (increase of 1.20 beats per minute in CYMBALTA - treated patients, decrease of 0.17 beats per minute in placebo-treated patients).

6.8 Laboratory Changes in Adults

CYMBALTA treatment in placebo-controlled clinical trials across approved indications, was associated with small mean increases from baseline to endpoint in ALT, AST, CPK, and alkaline phosphatase; infrequent, modest, transient, abnormal values were observed for these analytes in CYMBALTA-treated patients when compared with placebo-treated patients [see Warnings and Precautions (5.2)]. High bicarbonate, cholesterol, and abnormal (high or low) potassium, were observed more frequently in CYMBALTA treated patients compared to placebo.

6.9 Electrocardiogram Changes in Adults

The effect of CYMBALTA 160 mg and 200 mg administered twice daily to steady state was evaluated in a randomized, double-blinded, two-way crossover study in 117 healthy female subjects. No QT interval prolongation was detected. CYMBALTA appears to be associated with concentration-dependent but not clinically meaningful QT shortening.

6.10 Other Adverse Reactions Observed During the Premarketing and Postmarketing Clinical Trial Evaluation of CYMBALTA in Adults

Following is a list of treatment-emergent adverse reactions reported by patients treated with CYMBALTA in clinical trials. In clinical trials of all indications, 34,756 patients were treated with CYMBALTA. Of these, 26.9% (9337) took CYMBALTA for at least 6 months, and 12.4% (4317) for at least one year. The following listing is not intended to include reactions (1) already listed in previous tables or elsewhere in labeling, (2) for which a drug cause was remote, (3) which were so general as to be uninformative, (4) which were not considered to have significant clinical implications, or (5) which occurred at a rate equal to or less than placebo.

Reactions are categorized by body system according to the following definitions: frequent adverse reactions are those occurring in at least 1/100 patients; infrequent adverse reactions are those occurring in 1/100 to 1/1000 patients; rare reactions are those occurring in fewer than 1/1000 patients.

Cardiac Disorders — Frequent: palpitations; Infrequent: myocardial infarction and tachycardia.

Ear and Labyrinth Disorders — Frequent: vertigo; Infrequent: ear pain and tinnitus.

Endocrine Disorders — Infrequent: hypothyroidism.

Eye Disorders — Frequent: vision blurred; Infrequent: diplopia, dry eye, and visual impairment.

Gastrointestinal Disorders — Frequent: flatulence; Infrequent: dysphagia, eructation, gastritis, gastrointestinal hemorrhage, halitosis, and stomatitis; Rare: gastric ulcer.

General Disorders and Administration Site Conditions — Frequent: chills/rigors; Infrequent: falls, feeling abnormal, feeling hot and/or cold, malaise, and thirst; Rare: gait disturbance.

Infections and Infestations — Infrequent: gastroenteritis and laryngitis.

Investigations — Frequent: weight increased, weight decreased; Infrequent: blood cholesterol increased.

Metabolism and Nutrition Disorders — Infrequent: dehydration and hyperlipidemia; Rare: dyslipidemia.

Musculoskeletal and Connective Tissue Disorders — Frequent: musculoskeletal pain; Infrequent: muscle tightness and muscle twitching.

Nervous System Disorders — Frequent: dysgeusia, lethargy, and paraesthesia/hypoesthesia; Infrequent: disturbance in attention, dyskinesia, myoclonus, and poor quality sleep; Rare: dysarthria.

Psychiatric Disorders — Frequent: abnormal dreams and sleep disorder; Infrequent: apathy, bruxism, disorientation/confusional state, irritability, mood swings, and suicide attempt; Rare: completed suicide.

Renal and Urinary Disorders — Frequent: urinary frequency; Infrequent: dysuria, micturition urgency, nocturia, polyuria, and urine odor abnormal.

Reproductive System and Breast Disorders — Frequent: anorgasmia/orgasm abnormal; Infrequent: menopausal symptoms, sexual dysfunction, and testicular pain; Rare: menstrual disorder.

Respiratory, Thoracic and Mediastinal Disorders — Frequent: yawning, oropharyngeal pain; Infrequent: throat tightness.

Skin and Subcutaneous Tissue Disorders — Frequent: pruritus; Infrequent: cold sweat, dermatitis contact, erythema, increased tendency to bruise, night sweats, and photosensitivity reaction; Rare: ecchymosis.

Vascular Disorders — Frequent: hot flush; Infrequent: flushing, orthostatic hypotension, and peripheral coldness.

6.11 Adverse Reactions Observed in Children and Adolescent Placebo-Controlled Clinical Trials

The adverse drug reaction profile observed in pediatric clinical trials (children and adolescents) was consistent with the adverse drug reaction profile observed in adult clinical trials. The specific adverse drug reactions observed in adult patients can be expected to be observed in pediatric patients (children and adolescents) [see Adverse Reactions (6.5)]. The most common (≥5% and twice placebo) adverse reactions observed in pediatric clinical trials include: nausea, diarrhea, decreased weight, and dizziness.

Table 6 provides the incidence of treatment-emergent adverse reactions in MDD and GAD pediatric placebo-controlled trials that occurred in greater than 2% of patients treated with CYMBALTA and with an incidence greater than placebo.

Table 6: Treatment-Emergent Adverse Reactions: Incidence of 2% or More and Greater than Placebo in three 10-week Pediatric Placebo-Controlled Trialsa
 | Percentage of Pediatric Patients Reporting Reaction
System Organ Class/Adverse Reaction | CYMBALTA (N=476) | Placebo (N=362)
Gastrointestinal Disorders
Nausea | 18 | 8
Abdominal Painb | 13 | 10
Vomiting | 9 | 4
Diarrhea | 6 | 3
Dry Mouth | 2 | 1
General Disorders and Administration Site Conditions
Fatiguec | 7 | 5
Investigations
Decreased Weightd | 14 | 6
Metabolism and Nutrition Disorders
Decreased Appetite | 10 | 5
Nervous System Disorders
Headache | 18 | 13
Somnolencee | 11 | 6
Dizziness | 8 | 4
Psychiatric Disorders
Insomniaf | 7 | 4
Respiratory, Thoracic, and Mediastinal Disorders
Oropharyngeal Pain | 4 | 2
Cough | 3 | 1
a The inclusion of an event in the table is determined based on the percentages before rounding; however, the percentages displayed in the table are rounded to the nearest integer.
b Also includes abdominal pain upper, abdominal pain lower, abdominal tenderness, abdominal discomfort, and gastrointestinal pain.
c Also includes asthenia.
d Frequency based on weight measurement meeting potentially clinically significant threshold of ≥3.5% weight loss (N=467 CYMBALTA; N=354 Placebo).
e Also includes hypersomnia and sedation.
f Also includes initial insomnia, insomnia, middle insomnia, and terminal insomnia.

Other adverse reactions that occurred at an incidence of less than 2% but were reported by more CYMBALTA treated patients than placebo treated patients and are associated CYMBALTA treatment: abnormal dreams (including nightmare), anxiety, flushing (including hot flush), hyperhidrosis, palpitations, pulse increased, and tremor.

Discontinuation-emergent symptoms have been reported when stopping CYMBALTA. The most commonly reported symptoms following discontinuation of CYMBALTA in pediatric clinical trials have included headache, dizziness, insomnia, and abdominal pain [see Warnings and Precautions (5.7) and Adverse Reactions (6.2)].

Growth (Height and Weight) — Decreased appetite and weight loss have been observed in association with the use of SSRIs and SNRIs. Pediatric patients treated with CYMBALTA in clinical trials experienced a 0.1kg mean decrease in weight at 10 weeks, compared with a mean weight gain of approximately 0.9 kg in placebo-treated patients. The proportion of patients who experienced a clinically significant decrease in weight (≥3.5%) was greater in the CYMBALTA group than in the placebo group (14% and 6%, respectively). Subsequently, over the 4- to 6-month uncontrolled extension periods, CYMBALTA-treated patients on average trended toward recovery to their expected baseline weight percentile based on population data from age- and sex-matched peers. In studies up to 9 months, CYMBALTA-treated pediatric patients experienced an increase in height of 1.7 cm on average (2.2 cm increase in children [7 to 11 years of age] and 1.3 cm increase in adolescents [12 to 17 years of age]). While height increase was observed during these studies, a mean decrease of 1% in height percentile was observed (decrease of 2% in children [7 to 11 years of age] and increase of 0.3% in adolescents [12 to 17 years of age]). Weight and height should be monitored regularly in children and adolescents treated with CYMBALTA.

6.12 Postmarketing Spontaneous Reports

The following adverse reactions have been identified during post approval use of CYMBALTA. Because these reactions are reported voluntarily from a population of uncertain size, it is not always possible to reliably estimate their frequency or establish a causal relationship to drug exposure.

Adverse reactions reported since market introduction that were temporally related to CYMBALTA therapy and not mentioned elsewhere in labeling include: anaphylactic reaction, aggression and anger (particularly early in treatment or after treatment discontinuation), angioneurotic edema, angle-closure glaucoma, colitis (microscopic or unspecified), cutaneous vasculitis (sometimes associated with systemic involvement), extrapyramidal disorder, galactorrhea, gynecological bleeding, hallucinations, hyperglycemia, hyperprolactinemia, hypersensitivity, hypertensive crisis, muscle spasm, rash, restless legs syndrome, seizures upon treatment discontinuation, supraventricular arrhythmia, tinnitus (upon treatment discontinuation), trismus, and urticaria.

7 DRUG INTERACTIONS

Both CYP1A2 and CYP2D6 are responsible for duloxetine metabolism.

7.1 Inhibitors of CYP1A2

When duloxetine 60 mg was co-administered with fluvoxamine 100 mg, a potent CYP1A2 inhibitor, to male subjects (n=14) duloxetine AUC was increased approximately 6-fold, the Cmax was increased about 2.5-fold, and duloxetine t1/2 was increased approximately 3-fold. Other drugs that inhibit CYP1A2 metabolism include cimetidine and quinolone antimicrobials such as ciprofloxacin and enoxacin [see Warnings and Precautions (5.12)].

7.2 Inhibitors of CYP2D6

Concomitant use of duloxetine (40 mg once daily) with paroxetine (20 mg once daily) increased the concentration of duloxetine AUC by about 60%, and greater degrees of inhibition are expected with higher doses of paroxetine. Similar effects would be expected with other potent CYP2D6 inhibitors (e.g., fluoxetine, quinidine) [see Warnings and Precautions (5.12)].

7.3 Dual Inhibition of CYP1A2 and CYP2D6

Concomitant administration of duloxetine 40 mg twice daily with fluvoxamine 100 mg, a potent CYP1A2 inhibitor, to CYP2D6 poor metabolizer subjects (n=14) resulted in a 6-fold increase in duloxetine AUC and Cmax.

7.4 Drugs that Interfere with Hemostasis (e.g., NSAIDs, Aspirin, and Warfarin)

Serotonin release by platelets plays an important role in hemostasis. Epidemiological studies of the case-control and cohort design that have demonstrated an association between use of psychotropic drugs that interfere with serotonin reuptake and the occurrence of upper gastrointestinal bleeding have also shown that concurrent use of an NSAID or aspirin may potentiate this risk of bleeding. Altered anticoagulant effects, including increased bleeding, have been reported when SSRIs or SNRIs are co-administered with warfarin. Concomitant administration of warfarin (2-9 mg once daily) under steady state conditions with duloxetine 60 or 120 mg once daily for up to 14 days in healthy subjects (n=15) did not significantly change INR from baseline (mean INR changes ranged from 0.05 to +0.07). The total warfarin (protein bound plus free drug) pharmacokinetics (AUCτ,ss, Cmax,ss or tmax,ss) for both R- and S-warfarin were not altered by duloxetine. Because of the potential effect of duloxetine on platelets, patients receiving warfarin therapy should be carefully monitored when duloxetine is initiated or discontinued [see Warnings and Precautions (5.5)].

7.5 Lorazepam

Under steady-state conditions for duloxetine (60 mg Q 12 hours) and lorazepam (2 mg Q 12 hours), the pharmacokinetics of duloxetine were not affected by co-administration.

7.6 Temazepam

Under steady-state conditions for duloxetine (20 mg qhs) and temazepam (30 mg qhs), the pharmacokinetics of duloxetine were not affected by co-administration.

7.7 Drugs that Affect Gastric Acidity

CYMBALTA has an enteric coating that resists dissolution until reaching a segment of the gastrointestinal tract where the pH exceeds 5.5. In extremely acidic conditions, CYMBALTA, unprotected by the enteric coating, may undergo hydrolysis to form naphthol. Caution is advised in using CYMBALTA in patients with conditions that may slow gastric emptying (e.g., some diabetics). Drugs that raise the gastrointestinal pH may lead to an earlier release of duloxetine. However, co-administration of CYMBALTA with aluminum- and magnesium-containing antacids (51 mEq) or CYMBALTA with famotidine, had no significant effect on the rate or extent of duloxetine absorption after administration of a 40 mg oral dose. It is unknown whether the concomitant administration of proton pump inhibitors affects duloxetine absorption [see Warnings and Precautions (5.14)].

7.8 Drugs Metabolized by CYP1A2

In vitro drug interaction studies demonstrate that duloxetine does not induce CYP1A2 activity. Therefore, an increase in the metabolism of CYP1A2 substrates (e.g., theophylline, caffeine) resulting from induction is not anticipated, although clinical studies of induction have not been performed. Duloxetine is an inhibitor of the CYP1A2 isoform in in vitro studies, and in two clinical studies the average (90% confidence interval) increase in theophylline AUC was 7% (1%-15%) and 20% (13%-27%) when co-administered with duloxetine (60 mg twice daily).

7.9 Drugs Metabolized by CYP2D6

Duloxetine is a moderate inhibitor of CYP2D6. When duloxetine was administered (at a dose of 60 mg twice daily) in conjunction with a single 50 mg dose of desipramine, a CYP2D6 substrate, the AUC of desipramine increased 3-fold [see Warnings and Precautions (5.12)].

7.10 Drugs Metabolized by CYP2C9

Results of in vitro studies demonstrate that duloxetine does not inhibit activity. In a clinical study, the pharmacokinetics of S-warfarin, a CYP2C9 substrate, were not significantly affected by duloxetine [see Drug Interactions (7.4)].

7.11 Drugs Metabolized by CYP3A

Results of in vitro studies demonstrate that duloxetine does not inhibit or induce CYP3A activity. Therefore, an increase or decrease in the metabolism of CYP3A substrates (e.g., oral contraceptives and other steroidal agents) resulting from induction or inhibition is not anticipated, although clinical studies have not been performed.

7.12 Drugs Metabolized by CYP2C19

Results of in vitro studies demonstrate that duloxetine does not inhibit CYP2C19 activity at therapeutic concentrations. Inhibition of the metabolism of CYP2C19 substrates is therefore not anticipated, although clinical studies have not been performed.

7.13 Monoamine Oxidase Inhibitors (MAOIs)

[See Dosage and Administration (2.8, 2.9), Contraindications (4), and Warnings and Precautions (5.4)].

7.14 Serotonergic Drugs

[See Dosage and Administration (2.8, 2.9), Contraindications (4), and Warnings and Precautions (5.4)].

7.15 Alcohol

When CYMBALTA and ethanol were administered several hours apart so that peak concentrations of each would coincide, CYMBALTA did not increase the impairment of mental and motor skills caused by alcohol.

In the CYMBALTA clinical trials database, three CYMBALTA-treated patients had liver injury as manifested by ALT and total bilirubin elevations, with evidence of obstruction. Substantial intercurrent ethanol use was present in each of these cases, and this may have contributed to the abnormalities seen [see Warnings and Precautions (5.2, 5.12)].

7.16 CNS Drugs

[See Warnings and Precautions (5.12)].

7.17 Drugs Highly Bound to Plasma Protein

Because duloxetine is highly bound to plasma protein, administration of CYMBALTA to a patient taking another drug that is highly protein bound may cause increased free concentrations of the other drug, potentially resulting in adverse reactions. However, co-administration of duloxetine (60 or 120 mg) with warfarin (2-9 mg), a highly protein-bound drug, did not result in significant changes in INR and in the pharmacokinetics of either total S-or total R-warfarin (protein bound plus free drug) [see Drug Interactions (7.4)].

8 USE IN SPECIFIC POPULATIONS

8.1 Pregnancy

Pregnancy Category C

Pregnancy Exposure Registry — There is a pregnancy registry that monitors the pregnancy outcomes in women exposed to CYMBALTA during pregnancy. To enroll, contact the CYMBALTA Pregnancy Registry at 1-866-814-6975 or www.cymbaltapregnancyregistry.com.

Risk Summary — There are no adequate and well-controlled studies of CYMBALTA administration in pregnant women. In animal studies with duloxetine, fetal weights were decreased but there was no evidence of teratogenicity in pregnant rats and rabbits at oral doses administered during the period of organogenesis up to 4 and 7 times the maximum recommended human dose (MRHD) of 120 mg/day, respectively. When duloxetine was administered orally to pregnant rats throughout gestation and lactation, pup weights at birth and pup survival to 1 day postpartum were decreased at a dose 2 times the MRHD. At this dose, pup behaviors consistent with increased reactivity, such as increased startle response to noise and decreased habituation of locomotor activity were observed. Post-weaning growth was not adversely affected. CYMBALTA should be used in pregnancy only if the potential benefit justifies the potential risk to the fetus.

Clinical Considerations

Fetal/Neonatal Adverse Reaction — Neonates exposed during pregnancy to serotonin - norepinephrine reuptake inhibitors (SNRIs) or selective serotonin reuptake inhibitors (SSRIs) have developed complications requiring prolonged hospitalization, respiratory support, and tube feeding which can arise immediately upon delivery. Reported clinical findings have included respiratory distress, cyanosis, apnea, seizures, temperature instability, feeding difficulty, vomiting, hypoglycemia, hypotonia, hypertonia, hyperreflexia, tremor, jitteriness, irritability, and constant crying. These features are consistent with either a direct toxic effect of the SNRIs or SSRIs, or possibly, a drug discontinuation syndrome. It should be noted that, in some cases, the clinical picture is consistent with serotonin syndrome [see Warnings and Precautions (5.4)].

Data

Animal Data — In animal reproduction studies, duloxetine has been shown to have adverse effects on embryo/fetal and postnatal development.

When duloxetine was administered orally to pregnant rats and rabbits during the period of organogenesis, there was no evidence of teratogenicity at doses up to 45 mg/kg/day (4 times the maximum recommended human dose (MRHD) of 120 mg/day on a mg/m^2 basis, in rat; 7 times the MRHD in rabbit). However, fetal weights were decreased at this dose, with a no-effect dose of 10 mg/kg/day approximately equal to the MRHD in rats; 2 times the MRHD in rabbits).

When duloxetine was administered orally to pregnant rats throughout gestation and lactation, the survival of pups to 1 day postpartum and pup body weights at birth and during the lactation period were decreased at a dose of 30 mg/kg/day (2 times the MRHD); the no-effect dose was 10 mg/kg/day. Furthermore, behaviors consistent with increased reactivity, such as increased startle response to noise and decreased habituation of locomotor activity, were observed in pups following maternal exposure to 30 mg/kg/day. Post-weaning growth and reproductive performance of the progeny were not affected adversely by maternal duloxetine treatment.

8.3 Nursing Mothers

Risk Summary

CYMBALTA is present in human milk. In a published study, lactating women who were weaning their infants were given CYMBALTA. At steady state, the concentration of CYMBALTA in breast milk was approximately 25% that of maternal plasma. The estimated daily infant dose was approximately 0.14% of the maternal dose. The developmental and health benefits of human milk feeding should be considered along with the mother's clinical need for CYMBALTA and any potential adverse effects on the milk-fed child from the drug or from the underlying maternal condition. Exercise caution when CYMBALTA is administered to a nursing woman.

Data

The disposition of CYMBALTA was studied in 6 lactating women who were at least 12 weeks postpartum and had elected to wean their infants. The women were given 40 mg of CYMBALTA twice daily for 3.5 days. The peak concentration measured in breast milk occurred at a median of 3 hours after the dose. The amount of CYMBALTA in breast milk was approximately 7 mcg/day while on that dose; the estimated daily infant dose was approximately 2 mcg/kg/day. The presence of CYMBALTA metabolites in breast milk was not examined.

8.4 Pediatric Use

Generalized Anxiety Disorder — In pediatric patients aged 7 to 17 years, efficacy was demonstrated in one 10-week, placebo-controlled trial. The study included 272 pediatric patients with GAD of which 47% were 7 to 11 years of age. CYMBALTA demonstrated superiority over placebo as measured by greater improvement in the Pediatric Anxiety Rating Scale (PARS) for GAD severity score [see Clinical Studies (14.2)]. The safety and effectiveness in pediatric patients less than 7 years of age have not been established.

Major Depressive Disorder — Efficacy was not demonstrated in two 10-week, placebo-controlled trials with 800 pediatric patients with MDD, age 7-17. Neither CYMBALTA nor an active control (indicated for treatment of pediatric depression) was superior to placebo. The safety and effectiveness in pediatric patients less than 7 years of age have not been established.

The most frequently observed adverse reactions in the clinical trials included nausea, headache, decreased weight, and abdominal pain. Decreased appetite and weight loss have been observed in association with the use of SSRIs and SNRIs. Perform regular monitoring of weight and growth in children and adolescents treated with an SNRI such as CYMBALTA [see Adverse Reactions (6.11)].

Use of CYMBALTA in a child or adolescent must balance the potential risks with the clinical need [see Boxed Warning and Warnings and Precautions (5.1)].

Animal Data — Duloxetine administration to young rats from post-natal day 21 (weaning) through post-natal day 90 (adult) resulted in decreased body weights that persisted into adulthood, but recovered when drug treatment was discontinued; slightly delayed (~1.5 days) sexual maturation in females, without any effect on fertility; and a delay in learning a complex task in adulthood, which was not observed after drug treatment was discontinued. These effects were observed at the high dose of 45 mg/kg/day (2 times the MRHD, for a child); the no-effect-level was 20 mg/kg/day (≈1 times the MRHD, for a child).

8.5 Geriatric Use

Of the 2,418 patients in premarketing clinical studies of CYMBALTA for MDD, 5.9% (143) were 65 years of age or over. Of the 1041 patients in CLBP premarketing studies, 21.2% (221) were 65 years of age or over. Of the 487 patients in OA premarketing studies, 40.5% (197) were 65 years of age or over. Of the 1,074 patients in the DPNP premarketing studies, 33% (357) were 65 years of age or over. Of the 1,761 patients in FM premarketing studies, 7.9% (140) were 65 years of age or over. In the MDD, GAD, DPNP, FM, OA, and CLBP studies, no overall differences in safety or effectiveness were generally observed between these subjects and younger subjects, and other reported clinical experience has not identified differences in responses between the elderly and younger patients, but greater sensitivity of some older individuals cannot be ruled out. SSRIs and SNRIs, including CYMBALTA have been associated with cases of clinically significant hyponatremia in elderly patients, who may be at greater risk for this adverse event [see Warnings and Precautions (5.13)].

In an analysis of data from all placebo-controlled-trials, patients treated with CYMBALTA reported a higher rate of falls compared to patients treated with placebo. The increased risk appears to be proportional to a patient's underlying risk for falls. Underlying risk appears to increase steadily with age. As elderly patients tend to have a higher prevalence of risk factors for falls such as medications, medical comorbidities and gait disturbances, the impact of increasing age by itself on falls during treatment with CYMBALTA is unclear. Falls with serious consequences including bone fractures and hospitalizations have been reported [see Warnings and Precautions (5.3) and Adverse Reactions (6.10)].

The pharmacokinetics of duloxetine after a single dose of 40 mg were compared in healthy elderly females (65 to 77 years) and healthy middle-age females (32 to 50 years). There was no difference in the Cmax, but the AUC of duloxetine was somewhat (about 25%) higher and the half-life about 4 hours longer in the elderly females. Population pharmacokinetic analyses suggest that the typical values for clearance decrease by approximately 1% for each year of age between 25 to 75 years of age; but age as a predictive factor only accounts for a small percentage of between-patient variability. Dosage adjustment based on the age of the patient is not necessary.

8.6 Gender

Duloxetine's half-life is similar in men and women. Dosage adjustment based on gender is not necessary.

8.7 Smoking Status

Duloxetine bioavailability (AUC) appears to be reduced by about one-third in smokers. Dosage modifications are not recommended for smokers.

8.8 Race

No specific pharmacokinetic study was conducted to investigate the effects of race.

8.9 Hepatic Impairment

Patients with clinically evident hepatic impairment have decreased duloxetine metabolism and elimination. After a single 20 mg dose of CYMBALTA, 6 cirrhotic patients with moderate liver impairment (Child-Pugh Class B) had a mean plasma duloxetine clearance about 15% that of age- and gender-matched healthy subjects, with a 5-fold increase in mean exposure (AUC). Although Cmax was similar to normals in the cirrhotic patients, the half-life was about 3 times longer [see Dosage and Administration (2.6) and Warnings and Precautions (5.14)].

8.10 Severe Renal Impairment

Limited data are available on the effects of duloxetine in patients with end-stage renal disease (ESRD). After a single 60 mg dose of duloxetine, Cmax and AUC values were approximately 100% greater in patients with end-stage renal disease receiving chronic intermittent hemodialysis than in subjects with normal renal function. The elimination half-life, however, was similar in both groups. The AUCs of the major circulating metabolites, 4-hydroxy duloxetine glucuronide and 5-hydroxy, 6-methoxy duloxetine sulfate, largely excreted in urine, were approximately 7- to 9-fold higher and would be expected to increase further with multiple dosing. Population PK analyses suggest that mild to moderate degrees of renal impairment (estimated CrCl 30-80 mL/min) have no significant effect on duloxetine apparent clearance [see Dosage and Administration (2.6) and Warnings and Precautions (5.14)].

9 DRUG ABUSE AND DEPENDENCE

9.2 Abuse

In animal studies, duloxetine did not demonstrate barbiturate-like (depressant) abuse potential.

While CYMBALTA has not been systematically studied in humans for its potential for abuse, there was no indication of drug-seeking behavior in the clinical trials. However, it is not possible to predict on the basis of premarketing experience the extent to which a CNS active drug will be misused, diverted, and/or abused once marketed. Consequently, physicians should carefully evaluate patients for a history of drug abuse and follow such patients closely, observing them for signs of misuse or abuse of CYMBALTA (e.g., development of tolerance, incrementation of dose, drug-seeking behavior).

9.3 Dependence

In drug dependence studies, duloxetine did not demonstrate dependence-producing potential in rats.

10 OVERDOSAGE

10.1 Signs and Symptoms

In postmarketing experience, fatal outcomes have been reported for acute overdoses, primarily with mixed overdoses, but also with duloxetine only, at doses as low as 1000 mg. Signs and symptoms of overdose (duloxetine alone or with mixed drugs) included somnolence, coma, serotonin syndrome, seizures, syncope, tachycardia, hypotension, hypertension, and vomiting.

10.2 Management of Overdose

There is no specific antidote to CYMBALTA, but if serotonin syndrome ensues, specific treatment (such as with cyproheptadine and/or temperature control) may be considered. In case of acute overdose, treatment should consist of those general measures employed in the management of overdose with any drug.

An adequate airway, oxygenation, and ventilation should be assured, and cardiac rhythm and vital signs should be monitored. Induction of emesis is not recommended. Gastric lavage with a large-bore orogastric tube with appropriate airway protection, if needed, may be indicated if performed soon after ingestion or in symptomatic patients.

Activated charcoal may be useful in limiting absorption of duloxetine from the gastrointestinal tract. Administration of activated charcoal has been shown to decrease AUC and Cmax by an average of one-third, although some subjects had a limited effect of activated charcoal. Due to the large volume of distribution of this drug, forced diuresis, dialysis, hemoperfusion, and exchange transfusion are unlikely to be beneficial.

In managing overdose, the possibility of multiple drug involvement should be considered. A specific caution involves patients who are taking or have recently taken CYMBALTA and might ingest excessive quantities of a TCA. In such a case, decreased clearance of the parent tricyclic and/or its active metabolite may increase the possibility of clinically significant sequelae and extend the time needed for close medical observation [see Warnings and Precautions (5.4) and Drug Interactions (7)]. The physician should consider contacting a poison control center (1-800-222-1222 or www.poison.org) for additional information on the treatment of any overdose. Telephone numbers for certified poison control centers are listed in the Physicians' Desk Reference (PDR).

11 DESCRIPTION

CYMBALTA® (duloxetine delayed-release capsules) is a selective serotonin and norepinephrine reuptake inhibitor (SSNRI) for oral administration. Its chemical designation is (+)-(S)-N-methyl-γ-(1-naphthyloxy)-2-thiophenepropylamine hydrochloride. The empirical formula is C18H19NOS•HCl, which corresponds to a molecular weight of 333.88. The structural formula is:

Duloxetine hydrochloride is a white to slightly brownish white solid, which is slightly soluble in water.

Each capsule contains enteric-coated pellets of 22.4, 33.7, or 67.3 mg of duloxetine hydrochloride equivalent to 20, 30, or 60 mg of duloxetine, respectively. These enteric-coated pellets are designed to prevent degradation of the drug in the acidic environment of the stomach. Inactive ingredients include FD&C Blue No. 2, gelatin, hypromellose, hydroxypropyl methylcellulose acetate succinate, sodium lauryl sulfate, sucrose, sugar spheres, talc, titanium dioxide, and triethyl citrate. The 20 and 60 mg capsules also contain iron oxide yellow.

12 CLINICAL PHARMACOLOGY

12.1 Mechanism of Action

Although the exact mechanisms of the antidepressant, central pain inhibitory and anxiolytic actions of duloxetine in humans are unknown, these actions are believed to be related to its potentiation of serotonergic and noradrenergic activity in the CNS.

12.2 Pharmacodynamics

Preclinical studies have shown that duloxetine is a potent inhibitor of neuronal serotonin and norepinephrine reuptake and a less potent inhibitor of dopamine reuptake. Duloxetine has no significant affinity for dopaminergic, adrenergic, cholinergic, histaminergic, opioid, glutamate, and GABA receptors in vitro. Duloxetine does not inhibit monoamine oxidase (MAO).

CYMBALTA is in a class of drugs known to affect urethral resistance. If symptoms of urinary hesitation develop during treatment with CYMBALTA, consideration should be given to the possibility that they might be drug-related.

12.3 Pharmacokinetics

Duloxetine has an elimination half-life of about 12 hours (range 8 to 17 hours) and its pharmacokinetics are dose proportional over the therapeutic range. Steady-state plasma concentrations are typically achieved after 3 days of dosing. Elimination of duloxetine is mainly through hepatic metabolism involving two P450 isozymes, CYP1A2 and CYP2D6.

Absorption and Distribution — Orally administered duloxetine hydrochloride is well absorbed. There is a median 2 hour lag until absorption begins (Tlag), with maximal plasma concentrations (Cmax) of duloxetine occurring 6 hours post dose. Food does not affect the Cmax of duloxetine, but delays the time to reach peak concentration from 6 to 10 hours and it marginally decreases the extent of absorption (AUC) by about 10%. There is a 3 hour delay in absorption and a one-third increase in apparent clearance of duloxetine after an evening dose as compared to a morning dose.

The apparent volume of distribution averages about 1640 L. Duloxetine is highly bound (>90%) to proteins in human plasma, binding primarily to albumin and α1-acid glycoprotein. The interaction between duloxetine and other highly protein bound drugs has not been fully evaluated. Plasma protein binding of duloxetine is not affected by renal or hepatic impairment.

Metabolism and Elimination — Biotransformation and disposition of duloxetine in humans have been determined following oral administration of ^14C-labeled duloxetine. Duloxetine comprises about 3% of the total radiolabeled material in the plasma, indicating that it undergoes extensive metabolism to numerous metabolites. The major biotransformation pathways for duloxetine involve oxidation of the naphthyl ring followed by conjugation and further oxidation. Both CYP1A2 and CYP2D6 catalyze the oxidation of the naphthyl ring in vitro. Metabolites found in plasma include 4-hydroxy duloxetine glucuronide and 5-hydroxy, 6-methoxy duloxetine sulfate. Many additional metabolites have been identified in urine, some representing only minor pathways of elimination. Only trace (<1% of the dose) amounts of unchanged duloxetine are present in the urine. Most (about 70%) of the duloxetine dose appears in the urine as metabolites of duloxetine; about 20% is excreted in the feces. Duloxetine undergoes extensive metabolism, but the major circulating metabolites have not been shown to contribute significantly to the pharmacologic activity of duloxetine.

Children and Adolescents (ages 7 to 17 years) — Duloxetine steady-state plasma concentration was comparable in children (7 to 12 years of age), adolescents (13 to 17 years of age) and adults. The average steady-state duloxetine concentration was approximately 30% lower in the pediatric population (children and adolescents) relative to the adults. The model-predicted duloxetine steady state plasma concentrations in children and adolescents were mostly within the concentration range observed in adult patients and did not exceed the concentration range in adults.

13 NONCLINICAL TOXICOLOGY

13.1 Carcinogenesis, Mutagenesis, Impairment of Fertility

Carcinogenesis — Duloxetine was administered in the diet to mice and rats for 2 years.

In female mice receiving duloxetine at 140 mg/kg/day (6 times the maximum recommended human dose (MRHD) of 120 mg/day on a mg/m^2 basis), there was an increased incidence of hepatocellular adenomas and carcinomas. The no-effect dose was 50 mg/kg/day (2 times the MRHD). Tumor incidence was not increased in male mice receiving duloxetine at doses up to 100 mg/kg/day (4 times the MRHD).

In rats, dietary doses of duloxetine up to 27 mg/kg/day in females (2 times the MRHD) and up to 36 mg/kg/day in males (3 times the MRHD) did not increase the incidence of tumors.

Mutagenesis — Duloxetine was not mutagenic in the in vitro bacterial reverse mutation assay (Ames test) and was not clastogenic in an in vivo chromosomal aberration test in mouse bone marrow cells. Additionally, duloxetine was not genotoxic in an in vitro mammalian forward gene mutation assay in mouse lymphoma cells or in an in vitro unscheduled DNA synthesis (UDS) assay in primary rat hepatocytes, and did not induce sister chromatid exchange in Chinese hamster bone marrow in vivo.

Impairment of Fertility — Duloxetine administered orally to either male or female rats prior to and throughout mating at doses up to 45 mg/kg/day (4 times the MRHD) did not alter mating or fertility.

14 CLINICAL STUDIES

The efficacy of CYMBALTA has been established in the following adequate and well-controlled trials:

- Major Depressive Disorder (MDD): 4 short-term and 1 maintenance trial in adults [see Clinical Studies (14.1)].
- Generalized Anxiety Disorder (GAD): 3 short-term trials in adults, 1 maintenance trial in adults, and 1 short-term trial in children and adolescents [see Clinical Studies (14.2)].
- Diabetic Peripheral Neuropathic Pain (DPNP): Two 12-week trials in adults [see Clinical Studies (14.3)].
- Fibromyalgia (FM): Two trials in adults (one of 3 months duration and one of 6 months duration) [see Clinical Studies (14.4)].
- Chronic Musculoskeletal Pain: Two 12- to 13-week trials in adult patients with chronic low back pain (CLBP) and one 13-week trial in adult patients with chronic pain due to osteoarthritis [see Clinical Studies (14.5)].

14.1 Major Depressive Disorder

The efficacy of CYMBALTA as a treatment for depression was established in 4 randomized, double-blind, placebo-controlled, fixed-dose studies in adult outpatients (18 to 83 years) meeting DSM-IV criteria for major depression. In 2 studies, patients were randomized to CYMBALTA 60 mg once daily (N=123 and N=128, respectively) or placebo (N=122 and N=139, respectively) for 9 weeks; in the third study, patients were randomized to CYMBALTA 20 or 40 mg twice daily (N=86 and N=91, respectively) or placebo (N=89) for 8 weeks; in the fourth study, patients were randomized to CYMBALTA 40 or 60 mg twice daily (N=95 and N=93, respectively) or placebo (N=93) for 8 weeks. There is no evidence that doses greater than 60 mg/day confer additional benefits.

In all 4 studies, CYMBALTA demonstrated superiority over placebo as measured by improvement in the 17-item Hamilton Depression Rating Scale (HAMD-17) total score (Studies 1-4 in Table 7).

In all of these clinical studies, analyses of the relationship between treatment outcome and age, gender, and race did not suggest any differential responsiveness on the basis of these patient characteristics.

Table 7: Summary of the Primary Efficacy Results for Studies in Major Depressive Disorder
Study Number | Treatment Group | Primary Efficacy Measure: HAMD-17
Study Number | Treatment Group | Mean Baseline Score (SD) | LS Mean Change from Baseline (SE) | Placebo-subtracted Differencea (95% CI)
Study 1 | CYMBALTA (60 mg/day)b | 21.5 (4.10) | -10.9 (0.70) | -4.9 (-6.8, -2.9)
 | Placebo | 21.1 (3.71) | -6.1 (0.69) | --
Study 2 | CYMBALTA (60 mg/day)b | 20.3 (3.32) | -10.5 (0.71) | -2.2 (-4.0, -0.3)
 | Placebo | 20.5 (3.42) | -8.3 (0.67) | --
Study 3 | CYMBALTA (20 mg BID)b | 18.6 (5.85) | -7.4 (0.80) | -2.4 (-4.7, -0.2)
 | CYMBALTA (40 mg BID)b | 18.1 (4.52) | -8.6 (0.81) | -3.6 (-5.9, -1.4)
 | Placebo | 17.2 (5.11) | -5.0 (0.81) | --
Study 4 | CYMBALTA (40 mg BID)b | 19.9 (3.54) | -11.0 (0.49) | -2.2 (-3.6, -0.9)
 | CYMBALTA (60 mg BID)b | 20.2 (3.41) | -12.1 (0.49) | -3.3 (-4.7, -1.9)
 | Placebo | 19.9 (3.58) | -8.8 (0.50) | --
SD: standard deviation; SE: standard error; LS Mean: least-squares mean; CI: confidence interval, not adjusted for multiplicity in trials where multiple dose groups were included.
a Difference (drug minus placebo) in least-squares mean change from baseline.
b Doses statistically significantly superior to placebo.

In another study, 533 patients meeting DSM-IV criteria for MDD received CYMBALTA 60 mg once daily during an initial 12-week open-label treatment phase. Two hundred and seventy-eight patients who responded to open label treatment (defined as meeting the following criteria at weeks 10 and 12: a HAMD-17 total score ≤9, Clinical Global Impressions of Severity (CGI-S) ≤2, and not meeting the DSM-IV criteria for MDD) were randomly assigned to continuation of CYMBALTA at the same dose (N=136) or to placebo (N=142) for 6 months. Patients on CYMBALTA experienced a statistically significantly longer time to relapse of depression than did patients on placebo (Study 5 in Figure 1). Relapse was defined as an increase in the CGI-S score of ≥2 points compared with that obtained at week 12, as well as meeting the DSM-IV criteria for MDD at 2 consecutive visits at least 2 weeks apart, where the 2-week temporal criterion had to be satisfied at only the second visit. The effectiveness of CYMBALTA in hospitalized patients with major depressive disorder has not been studied.

Figure 1: Kaplan-Meier Estimation of Cumulative Proportion of Patients with Relapse (MDD Study 5)

14.2 Generalized Anxiety Disorder

The efficacy of CYMBALTA in the treatment of generalized anxiety disorder (GAD) was established in 1 fixed-dose randomized, double-blind, placebo-controlled trial and 2 flexible-dose randomized, double-blind, placebo-controlled trials in adult outpatients between 18 and 83 years of age meeting the DSM-IV criteria for GAD.

In 1 flexible-dose study and in the fixed-dose study, the starting dose was 60 mg once daily where down titration to 30 mg once daily was allowed for tolerability reasons before increasing it to 60 mg once daily. Fifteen percent of patients were down titrated. One flexible-dose study had a starting dose of 30 mg once daily for 1 week before increasing it to 60 mg once daily.

The 2 flexible-dose studies involved dose titration with CYMBALTA doses ranging from 60 mg once daily to 120 mg once daily (N=168 and N=162) compared to placebo (N=159 and N=161) over a 10-week treatment period. The mean dose for completers at endpoint in the flexible-dose studies was 104.75 mg/day. The fixed-dose study evaluated CYMBALTA doses of 60 mg once daily (N=168) and 120 mg once daily (N=170) compared to placebo (N=175) over a 9-week treatment period. While a 120 mg/day dose was shown to be effective, there is no evidence that doses greater than 60 mg/day confer additional benefit.

In all 3 studies, CYMBALTA demonstrated superiority over placebo as measured by greater improvement in the Hamilton Anxiety Scale (HAM-A) total score (Studies 1-3 in Table 8) and by the Sheehan Disability Scale (SDS) global functional impairment score. The SDS is a composite measurement of the extent emotional symptoms disrupt patient functioning in 3 life domains: work/school, social life/leisure activities, and family life/home responsibilities.

In another study, 887 patients meeting DSM-IV-TR criteria for GAD received CYMBALTA 60 mg to 120 mg once daily during an initial 26-week open-label treatment phase. Four hundred and twenty-nine patients who responded to open-label treatment (defined as meeting the following criteria at weeks 24 and 26: a decrease from baseline HAM-A total score by at least 50% to a score no higher than 11, and a Clinical Global Impressions of Improvement [CGI-Improvement] score of 1 or 2) were randomly assigned to continuation of CYMBALTA at the same dose (N=216) or to placebo (N=213) and were observed for relapse. Of the patients randomized, 73% had been in a responder status for at least 10 weeks. Relapse was defined as an increase in CGI-Severity score at least 2 points to a score ≥4 and a MINI (Mini-International Neuropsychiatric Interview) diagnosis of GAD (excluding duration), or discontinuation due to lack of efficacy. Patients taking CYMBALTA experienced a statistically significantly longer time to relapse of GAD than did patients taking placebo (Study 4 in Figure 2).

Subgroup analyses did not indicate that there were any differences in treatment outcomes as a function of age or gender.

The efficacy of CYMBALTA in the treatment of patients ≥65 years of age with generalized anxiety disorder was established in one 10-week flexible-dose, randomized, double-blind, placebo-controlled trial in adults ≥65 years of age meeting the DSM-IV criteria for GAD. In this study, the starting dose was 30 mg once daily for 2 weeks before further dose increases in 30 mg increments at treatment weeks 2, 4, and 7 up to 120 mg once daily were allowed based on investigator judgment of clinical response and tolerability. The mean dose for patients completing the 10-week acute treatment phase was 50.95 mg. Patients treated with CYMBALTA (N=151) demonstrated significantly greater improvement compared with placebo (N=140) on mean change from baseline to endpoint as measured by the Hamilton Anxiety Rating Scale total score (Study 5 in Table 8).

The efficacy of CYMBALTA in the treatment of pediatric patients 7 to 17 years of age with generalized anxiety disorder (GAD) was established in 1 flexible-dose randomized, double-blind, placebo-controlled trial in pediatric outpatients with GAD (based on DSM-IV criteria).

In this study, the starting dose was 30 mg once daily for 2 weeks. Further dose increases in 30 mg increments up to 120 mg once daily were allowed based on investigator judgment of clinical response and tolerability. The mean dose for patients completing the 10-week treatment phase was 57.6 mg/day. In this study, CYMBALTA (N=135) demonstrated superiority over placebo (N=137) from baseline to endpoint as measured by greater improvement in the Pediatric Anxiety Rating Scale (PARS) for GAD severity score (Study 6 in Table 8).

Table 8: Summary of the Primary Efficacy Results for Studies in General Anxiety Disorder
Study Number | Treatment Group | Primary Efficacy Measure
Study Number | Treatment Group | Mean Baseline Score (SD) | LS Mean Change from Baseline (SE) | Placebo-subtracted Differencea (95% CI)
Study 1 (HAM-A) | CYMBALTA (60 mg/day)b | 25.1 (7.18) | -12.8 (0.68) | -4.4 (-6.2, -2.5)
Study 1 (HAM-A) | CYMBALTA (120 mg/day)b | 25.1 (7.24) | -12.5 (0.67) | -4.1 (-5.9, -2.3)
Study 1 (HAM-A) | Placebo | 25.8 (7.66) | -8.4 (0.67) | --
Study 2 (HAM-A) | CYMBALTA (60-120 mg/day)b | 22.5 (7.44) | -8.1 (0.70) | -2.2 (-4.2, -0.3)
Study 2 (HAM-A) | Placebo | 23.5 (7.91) | -5.9 (0.70) | --
Study 3 (HAM-A) | CYMBALTA (60-120 mg/day)b | 25.8 (5.66) | -11.8 (0.69) | -2.6 (-4.5, -0.7)
Study 3 (HAM-A) | Placebo | 25.0 (5.82) | -9.2 (0.67) | --
Study 5 (Elderly) (HAM-A) | CYMBALTA (60-120 mg/day)b | 24.6 (6.21) | -15.9 (0.63) | -4.2 (-5.9, -2.5)
Study 5 (Elderly) (HAM-A) | Placebo | 24.5 (7.05) | -11.7 (0.67) | --
Study 6 (Pediatric) | CYMBALTA (30-120 mg/day)b | 17.5 (1.98) | -9.7 (0.50) | -2.7 (-4.0, -1.3)
(PARS for GAD) | Placebo | 17.4 (2.24) | -7.1 (0.50) | --
SD: standard deviation; SE: standard error; LS Mean: least-squares mean; CI: confidence interval, not adjusted for multiplicity in trials where multiple dose groups were included.
a Difference (drug minus placebo) in least squares mean change from baseline.
b Dose statistically significantly superior to placebo.

Figure 2: Kaplan-Meier Estimation of Cumulative Proportion of Patients with Relapse (GAD Study 4)

14.3 Diabetic Peripheral Neuropathic Pain

The efficacy of CYMBALTA for the management of neuropathic pain associated with diabetic peripheral neuropathy was established in 2 randomized, 12-week, double-blind, placebo-controlled, fixed-dose studies in adult patients having diabetic peripheral neuropathic pain for at least 6 months. Study DPNP-1 and Study DPNP-2 enrolled a total of 791 patients of whom 592 (75%) completed the studies. Patients enrolled had Type I or II diabetes mellitus with a diagnosis of painful distal symmetrical sensorimotor polyneuropathy for at least 6 months. The patients had a baseline pain score of ≥4 on an 11-point scale ranging from 0 (no pain) to 10 (worst possible pain). Patients were permitted up to 4 g of acetaminophen per day as needed for pain, in addition to CYMBALTA. Patients recorded their pain daily in a diary.

Both studies compared CYMBALTA 60 mg once daily or 60 mg twice daily with placebo. DPNP-1 additionally compared CYMBALTA 20 mg with placebo. A total of 457 patients (342 CYMBALTA, 115 placebo) were enrolled in DPNP-1 and a total of 334 patients (226 CYMBALTA, 108 placebo) were enrolled in DPNP-2. Treatment with CYMBALTA 60 mg one or two times a day statistically significantly improved the endpoint mean pain scores from baseline and increased the proportion of patients with at least a 50% reduction in pain scores from baseline. For various degrees of improvement in pain from baseline to study endpoint, Figures 3 and 4 show the fraction of patients achieving that degree of improvement. The figures are cumulative, so that patients whose change from baseline is, for example, 50%, are also included at every level of improvement below 50%. Patients who did not complete the study were assigned 0% improvement. Some patients experienced a decrease in pain as early as week 1, which persisted throughout the study.

Figure 3: Percentage of Patients Achieving Various Levels of Pain Relief as Measured by 24-Hour Average Pain Severity - DPNP-1
Figure 4: Percentage of Patients Achieving Various Levels of Pain Relief as Measured by 24-Hour Average Pain Severity - DPNP-2

14.4 Fibromyalgia

The efficacy of CYMBALTA for the management of fibromyalgia was established in two randomized, double-blind, placebo-controlled, fixed-dose studies in adult patients meeting the American College of Rheumatology criteria for fibromyalgia (a history of widespread pain for 3 months, and pain present at 11 or more of the 18 specific tender point sites). Study FM-1 was three months in duration and enrolled female patients only. Study FM-2 was six months in duration and enrolled male and female patients. Approximately 25% of participants had a comorbid diagnosis of major depressive disorder (MDD). FM-1 and FM-2 enrolled a total of 874 patients of whom 541 (62%) completed the studies. The patients had a baseline pain score of 6.5 on an 11-point scale ranging from 0 (no pain) to 10 (worse possible pain).

Both studies compared CYMBALTA 60 mg once daily or 120 mg daily (given in divided doses in FM-1 and as a single daily dose in FM-2) with placebo. FM-2 additionally compared CYMBALTA 20 mg with placebo during the initial three months of a six-month study. A total of 354 patients (234 CYMBALTA, 120 placebo) were enrolled in FM-1 and a total of 520 patients (376 CYMBALTA, 144 placebo) were enrolled in FM-2 (5% male, 95% female). Treatment with CYMBALTA 60 mg or 120 mg daily statistically significantly improved the endpoint mean pain scores from baseline and increased the proportion of patients with at least a 50% reduction in pain score from baseline. Pain reduction was observed in patients both with and without comorbid MDD. However, the degree of pain reduction may be greater in patients with comorbid MDD. For various degrees of improvement in pain from baseline to study endpoint, Figures 5 and 6 show the fraction of patients achieving that degree of improvement. The figures are cumulative so that patients whose change from baseline is, for example, 50%, are also included at every level of improvement below 50%. Patients who did not complete the study were assigned 0% improvement. Some patients experienced a decrease in pain as early as week 1, which persisted throughout the study. Improvement was also demonstrated on measures of function (Fibromyalgia Impact Questionnaires) and patient global impression of change (PGI). Neither study demonstrated a benefit of 120 mg compared to 60 mg, and a higher dose was associated with more adverse reactions and premature discontinuations of treatment.

Figure 5: Percentage of Patients Achieving Various Levels of Pain Relief as Measured by 24-Hour Average Pain Severity - FM-1
Figure 6: Percentage of Patients Achieving Various Levels of Pain Relief as Measured by 24-Hour Average Pain Severity - FM-2

Additionally, the benefit of up-titration in non-responders to CYMBALTA at 60 mg/day was evaluated in a separate study. Patients were initially treated with CYMBALTA 60 mg once daily for eight weeks in open-label fashion. Subsequently, completers of this phase were randomized to double-blind treatment with CYMBALTA at either 60 mg once daily or 120 mg once daily. Those patients who were considered non-responders, where response was defined as at least a 30% reduction in pain score from baseline at the end of the 8-week treatment, were no more likely to meet response criteria at the end of 60 weeks of treatment if blindly titrated to CYMBALTA 120 mg as compared to those who were blindly continued on CYMBALTA 60 mg.

14.5 Chronic Musculoskeletal Pain

CYMBALTA is indicated for the management of chronic musculoskeletal pain. This has been established in studies in patients with chronic low back pain and chronic pain due to osteoarthritis.

Studies in Chronic Low Back Pain

The efficacy of CYMBALTA in chronic low back pain (CLBP) was assessed in two double-blind, placebo-controlled, randomized clinical trials of 13-weeks duration (Study CLBP-1 and Study CLBP-2), and one of 12-weeks duration (CLBP-3). CLBP-1 and CLBP-3 demonstrated efficacy of CYMBALTA in the treatment of chronic low back pain. Patients in all studies had no signs of radiculopathy or spinal stenosis.

Study CLBP-1: Two hundred thirty-six adult patients (N=115 on CYMBALTA, N=121 on placebo) enrolled and 182 (77%) completed 13-week treatment phase. After 7 weeks of treatment, CYMBALTA patients with less than 30% reduction in average daily pain and who were able to tolerate CYMBALTA 60 mg once daily had their dose of CYMBALTA, in a double-blinded fashion, increased to 120 mg once daily for the remainder of the study. Patients had a mean baseline pain rating of 6 on a numerical rating scale ranging from 0 (no pain) to 10 (worst possible pain). After 13 weeks of treatment, patients taking CYMBALTA 60-120 mg daily had a significantly greater pain reduction compared to placebo. Randomization was stratified by the patients' baseline NSAIDs-use status. Subgroup analyses did not indicate that there were differences in treatment outcomes as a function of NSAIDs use.

Study CLBP-2: Four hundred and four patients were randomized to receive fixed doses of CYMBALTA daily or a matching placebo (N=59 on CYMBALTA 20 mg, N=116 on CYMBALTA 60 mg, N=112 on CYMBALTA 120 mg, N=117 on placebo) and 267 (66%) completed the entire 13-week study. After 13 weeks of treatment, none of the three CYMBALTA doses showed a statistically significant difference in pain reduction compared to placebo.

Study CLBP-3: Four hundred and one patients were randomized to receive fixed doses of CYMBALTA 60 mg daily or placebo (N=198 on CYMBALTA, N=203 on placebo), and 303 (76%) completed the study. Patients had a mean baseline pain rating of 6 on a numerical rating scale ranging from 0 (no pain) to 10 (worst possible pain). After 12 weeks of treatment, patients taking CYMBALTA 60 mg daily had significantly greater pain reduction compared to placebo.

For various degrees of improvement in pain from baseline to study endpoint, Figures 7 and 8 show the fraction of patients in CLBP-1 and CLBP-3 achieving that degree of improvement. The figures are cumulative, so that patients whose change from baseline is, for example, 50%, are also included at every level of improvement below 50%. Patients who did not complete the study were assigned the value of 0% improvement.

Figure 7: Percentage of Patients Achieving Various Levels of Pain Relief as Measured by 24-Hour Average Pain Severity – CLBP-1
Figure 8: Percentage of Patients Achieving Various Levels of Pain Relief as Measured by 24-Hour Average Pain Severity – CLBP-3

Studies in Chronic Pain Due to Osteoarthritis

The efficacy of CYMBALTA in chronic pain due to osteoarthritis was assessed in 2 double-blind, placebo-controlled, randomized clinical trials of 13-weeks duration (Study OA-1 and Study OA-2). All patients in both studies fulfilled the ACR clinical and radiographic criteria for classification of idiopathic osteoarthritis of the knee. Randomization was stratified by the patients' baseline NSAIDs-use status. Patients assigned to CYMBALTA started treatment in both studies at a dose of 30 mg once daily for one week. After the first week, the dose of CYMBALTA was increased to 60 mg once daily. After 7 weeks of treatment with CYMBALTA 60 mg once daily, in OA-1 patients with sub-optimal response to treatment (<30% pain reduction) and tolerated CYMBALTA 60 mg once daily had their dose increased to 120 mg. However, in OA-2, all patients, regardless of their response to treatment after 7 weeks, were re-randomized to either continue receiving CYMBALTA 60 mg once daily or have their dose increased to 120 mg once daily for the remainder of the study. Patients in the placebo treatment groups in both studies received a matching placebo for the entire duration of studies. For both studies, efficacy analyses were conducted using 13-week data from the combined CYMBALTA 60 mg and 120 mg once daily treatment groups compared to the placebo group.

Study OA-1: Two hundred fifty-six patients (N=128 on CYMBALTA, N=128 on placebo) enrolled and 204 (80%) completed the study. Patients had a mean baseline pain rating of 6 on a numerical rating scale ranging from 0 (no pain) to 10 (worst possible pain). After 13 weeks of treatment, patients taking CYMBALTA had significantly greater pain reduction. Subgroup analyses did not indicate that there were differences in treatment outcomes as a function of NSAIDs use.

Study OA-2: Two hundred thirty-one patients (N=111 on CYMBALTA, N=120 on placebo) enrolled and 173 (75%) completed the study. Patients had a mean baseline pain of 6 on a numerical rating scale ranging from 0 (no pain) to 10 (worst possible pain). After 13 weeks of treatment, patients taking CYMBALTA did not show a significantly greater pain reduction.

In Study OA-1, for various degrees of improvement in pain from baseline to study endpoint, Figure 7 shows the fraction of patients achieving that degree of improvement. The figure is cumulative, so that patients whose change from baseline is, for example, 50%, are also included at every level of improvement below 50%. Patients who did not complete the study were assigned the value of 0% improvement.

Figure 9: Percentage of Patients Achieving Various Levels of Pain Relief as Measured by 24-Hour Average Pain Severity – OA-1

HOW SUPPLIED

Product: 68151-4679

NDC: 68151-4679-3 1 CAPSULE, DELAYED RELEASE in a PACKAGE

17 PATIENT COUNSELING INFORMATION

See FDA-approved patient labeling (Medication Guide).

- Information on Medication Guide — Inform patients, their families, and their caregivers about the benefits and risks associated with treatment with CYMBALTA and counsel them in its appropriate use. A patient Medication Guide is available for CYMBALTA. Instruct patients, their families, and their caregivers to read the Medication Guide before starting CYMBALTA and each time their prescription is renewed, and assist them in understanding its contents. Give patients the opportunity to discuss the contents of the Medication Guide and to obtain answers to any questions they may have. The complete text of the Medication Guide is reprinted at the end of this document.
  Advise patients of the following issues and ask them to alert their prescriber if these occur while taking CYMBALTA.
- Suicidal Thoughts and Behaviors — Encourage patients, their families, and their caregivers to be alert to the emergence of anxiety, agitation, panic attacks, insomnia, irritability, hostility, aggressiveness, impulsivity, akathisia (psychomotor restlessness), hypomania, mania, other unusual changes in behavior, worsening of depression, and suicidal ideation, especially early during antidepressant treatment and when the dose is adjusted up or down.
  Advise families and caregivers of patients to observe for the emergence of such symptoms on a day-to-day basis, since changes may be abrupt. Such symptoms should be reported to the patient's prescriber or health professional, especially if they are severe, abrupt in onset, or were not part of the patient's presenting symptoms. Symptoms such as these may be associated with an increased risk for suicidal thinking and behavior and indicate a need for very close monitoring and possibly changes in the medication [see Boxed Warning, and Warnings and Precautions (5.1)].
- CYMBALTA should be swallowed whole and should not be chewed or crushed, nor should the capsule be opened and its contents be sprinkled on food or mixed with liquids. All of these might affect the enteric coating.
- Continuing the Therapy Prescribed — While patients may notice improvement with CYMBALTA therapy in 1 to 4 weeks, advise patients to continue therapy as directed.
- Hepatotoxicity — Inform patients that severe liver problems, sometimes fatal, have been reported in patients treated with CYMBALTA. Instruct patients to talk to their healthcare provider if they develop itching, right upper belly pain, dark urine, or yellow skin/eyes while taking CYMBALTA, which may be signs of liver problems. Instruct patients to talk to their healthcare provider about their alcohol consumption. Use of CYMBALTA with heavy alcohol intake may be associated with severe liver injury [see Warnings and Precautions (5.2)].
- Alcohol — Although CYMBALTA does not increase the impairment of mental and motor skills caused by alcohol, use of CYMBALTA concomitantly with heavy alcohol intake may be associated with severe liver injury. For this reason, CYMBALTA should not be prescribed for patients with substantial alcohol use [see Warnings and Precautions (5.2) and Drug Interactions (7.15)].
- Orthostatic Hypotension, Falls and Syncope — Advise patients of the risk of orthostatic hypotension, falls and syncope, especially during the period of initial use and subsequent dose escalation, and in association with the use of concomitant drugs that might potentiate the orthostatic effect of CYMBALTA [see Warnings and Precautions (5.3)].
- Serotonin Syndrome — Caution patients about the risk of serotonin syndrome with the concomitant use of CYMBALTA and other serotonergic agents including triptans, tricyclic antidepressants, fentanyl, lithium, tramadol, buspirone, tryptophan and St. John's Wort [see Contraindications (4), Warnings and Precautions (5.4), and Drug Interactions (7.14)].
  Advise patients of the signs and symptoms associated with serotonin syndrome that may include mental status changes (e.g., agitation, hallucinations, delirium, and coma), autonomic instability (e.g., tachycardia, labile blood pressure, dizziness, diaphoresis, flushing, hyperthermia), neuromuscular changes (e.g., tremor, rigidity, myoclonus, hyperreflexia, incoordination), seizures, and/or gastrointestinal symptoms (e.g., nausea, vomiting, diarrhea). Caution patients to seek medical care immediately if they experience these symptoms.
- Abnormal Bleeding — Caution patients about the concomitant use of CYMBALTA and NSAIDs, aspirin, warfarin, or other drugs that affect coagulation since combined use of psychotropic drugs that interfere with serotonin reuptake and these agents has been associated with an increased risk of bleeding [see Warnings and Precautions (5.5)].
- Severe Skin Reactions — Caution patients that CYMBALTA may cause serious skin reactions. This may need to be treated in a hospital and may be life-threatening. Counsel patients to call their doctor right away or get emergency help if they have skin blisters, peeling rash, sores in their mouth, hives, or any other allergic reactions [see Warnings and Precautions (5.6)].
- Discontinuation of Treatment — Instruct patients that discontinuation of CYMBALTA may be associated with symptoms such as dizziness, headache, nausea, diarrhea, paresthesia, irritability, vomiting, insomnia, anxiety, hyperhidrosis, and fatigue, and should be advised not to alter their dosing regimen, or stop taking CYMBALTA without consulting their physician [see Warnings and Precautions (5.7)].
- Activation of Mania or Hypomania — Adequately screen patients with depressive symptoms for risk of bipolar disorder (e.g. family history of suicide, bipolar disorder, and depression) prior to initiating treatment with CYMBALTA. Advise patients to report any signs or symptoms of a manic reaction such as greatly increased energy, severe trouble sleeping, racing thoughts, reckless behavior, talking more or faster than usual, unusually grand ideas, and excessive happiness or irritability [see Warnings and Precautions (5.8)].
- Angle-Closure Glaucoma — Advise patients that taking CYMBALTA can cause mild pupillary dilation, which in susceptible individuals, can lead to an episode of angle-closure glaucoma. Pre-existing glaucoma is almost always open-angle glaucoma because angle-closure glaucoma, when diagnosed, can be treated definitively with iridectomy. Open-angle glaucoma is not a risk factor for angle-closure glaucoma. Patients may wish to be examined to determine whether they are susceptible to angle-closure, and have a prophylactic procedure (e.g., iridectomy), if they are susceptible. [See Warnings and Precautions (5.9)].
- Seizures — Advise patients to inform their physician if they have a history of seizure disorder [see Warnings and Precautions (5.10)].
- Effects on Blood Pressure — Caution patients that CYMBALTA may cause an increase in blood pressure [see Warnings and Precautions (5.11)].
- Concomitant Medications — Advise patients to inform their physicians if they are taking, or plan to take, any prescription or over-the-counter medications, since there is a potential for interactions [see Dosage and Administration (2.8, 2.9), Contraindications (4), Warnings and Precautions (5.4, 5.12), and Drug Interactions (7)].
- Hyponatremia — Advise patients that hyponatremia has been reported as a result of treatment with SNRIs and SSRIs, including CYMBALTA. Advise patients of the signs and symptoms of hyponatremia [see Warnings and Precautions (5.13)].
- Concomitant Illnesses — Advise patients to inform their physicians about all of their medical conditions [see Warnings and Precautions (5.14)].
- CYMBALTA is in a class of medicines that may affect urination. Instruct patients to consult with their healthcare provider if they develop any problems with urine flow [see Warnings and Precautions (5.15)].
- Pregnancy and Nursing Mothers
  Advise patients to notify their physician if they:
  - become pregnant during therapy
  - intend to become pregnant during therapy
  - are nursing [see Use in Specific Populations (8.1, 8.3)].
- Pediatric Use — Safety and efficacy of CYMBALTA in patients 7 to 17 years of age have been established for the treatment of GAD. The types of adverse reactions observed with CYMBALTA in children and adolescents were generally similar to those observed in adults. The safety and effectiveness of CYMBALTA have not been established in pediatric patients less than 18 years of age with other indications. [See Use in Specific Populations (8.4)].
- Interference with Psychomotor Performance — Any psychoactive drug may impair judgment, thinking, or motor skills. Although in controlled studies CYMBALTA has not been shown to impair psychomotor performance, cognitive function, or memory, it may be associated with sedation and dizziness. Therefore, caution patients about operating hazardous machinery including automobiles, until they are reasonably certain that CYMBALTA therapy does not affect their ability to engage in such activities.

Literature revised June 2015

Marketed by: Lilly USA, LLC, Indianapolis, IN 46285, USA
Copyright © 2004, 2015, Eli Lilly and Company. All rights reserved.

CYM-0006-USPI-20150618

Medication Guide

Cymbalta®
[sim-BALL-tah]
(duloxetine delayed-release capsules)

Read this Medication Guide before you start taking Cymbalta® and each time you get a refill. There may be new information. This information does not take the place of talking to your healthcare provider about your medical condition or treatment.

Talk to your healthcare provider about:

- all risks and benefits of treatment with antidepressant medicines
- all treatment choices for depression or other serious mental illness

What is the most important information I should know about antidepressant medicines, depression, other serious mental illnesses, and suicidal thoughts or actions?

1. Cymbalta and other antidepressant medicines may increase suicidal thoughts or actions in some children, teenagers, or young adults within the first few months of treatment or when the dose is changed.

2. Depression and other serious mental illnesses are the most important causes of suicidal thoughts or actions. Some people may have a particularly high risk of having suicidal thoughts or actions. These include people who have (or have a family history of) bipolar illness (also called manic-depressive illness).

3. How can I watch for and try to prevent suicidal thoughts and actions?

- Pay close attention to any changes in mood, behavior, actions, thoughts, or feelings, especially sudden changes. This is very important when an antidepressant medicine is started or when the dose is changed.
- Call your healthcare provider right away to report new or sudden changes in mood, behavior, thoughts, or feelings.
  - Keep all follow-up visits with your healthcare provider as scheduled. Call your healthcare provider between visits as needed, especially if you have concerns about symptoms.

Call your healthcare provider right away if you have any of the following symptoms or feelings, especially if they are new, worse, or worry you. In an emergency, call 911.

- attempts to commit suicide
- acting on dangerous impulses
- acting aggressive, being angry, or violent
- thoughts about suicide or dying
- new or worse depression
- new or worse anxiety
- panic attacks
- feeling very agitated or restless
- new or worse irritability
- trouble sleeping
- an extreme increase in activity or talking (mania)
- other unusual changes in behavior or mood

What else do I need to know about antidepressant medicines?

- Never stop an antidepressant medicine without first talking to a healthcare provider. Stopping an antidepressant medicine suddenly can cause other symptoms.
- Antidepressants are medicines used to treat depression and other illnesses. It is important to discuss all the risks of treating depression and also the risks of not treating it. Patients should discuss all treatment choices with your healthcare provider, not just the use of antidepressants.
- Antidepressant medicines have other side effects. Talk to your healthcare provider about the side effects of the medicine prescribed for you or your family member.
- Antidepressant medicines can interact with other medicines. Know all of the medicines that you or your family member takes. Keep a list of all medicines to show your healthcare provider. Do not start new medicines without first checking with your healthcare provider.

What is Cymbalta?

Cymbalta is a prescription medicine used to treat a certain type of depression called Major Depressive Disorder (MDD). Cymbalta belongs to a class of medicines known as SNRIs (or serotonin-norepinephrine reuptake inhibitors).

Cymbalta is also used to treat or manage:

- Generalized Anxiety Disorder (GAD)
- Diabetic Peripheral Neuropathic Pain (DPNP)
- Fibromyalgia (FM)
- Chronic Musculoskeletal Pain

Who should not take Cymbalta?

Do Not take Cymbalta if you:

- take a Monoamine Oxidase Inhibitor (MAOI). Ask your healthcare provider or pharmacist if you are not sure if you take an MAOI, including the antibiotic linezolid or intravenous methylene blue.
  - Do not take an MAOI within 5 days of stopping Cymbalta unless directed to do so by your healthcare provider.
  - Do not start Cymbalta if you stopped taking an MAOI in the last 14 days unless directed to do so by your healthcare provider.

People who take Cymbalta close in time to an MAOI may have a serious problem called Serotonin Syndrome (see “What are the possible side effects of Cymbalta?”).

What should I tell my healthcare provider before taking Cymbalta?

Before starting Cymbalta, tell your healthcare provider if you:

- have heart problems or high blood pressure
- have diabetes (Cymbalta treatment makes it harder for some people with diabetes to control their blood sugar)
- have liver problems
- have kidney problems
- have glaucoma
- have or had seizures or convulsions
- have bipolar disorder or mania
- have low sodium levels in your blood
- have delayed stomach emptying
- have or had bleeding problems
- are pregnant or plan to become pregnant. It is not known if Cymbalta will harm your unborn baby. Talk to your healthcare provider about the benefits and risks of treating depression or other conditions with Cymbalta during pregnancy.
  - If you become pregnant while taking Cymbalta, talk to your healthcare provider about registering with the Cymbalta Pregnancy Registry. You can register by calling 1-866-814-6975 or by visiting www.cymbaltapregnancyregistry.com. The purpose of this registry is to monitor the pregnancy outcomes in women who have been treated with Cymbalta at any time during pregnancy.
- are breastfeeding or plan to breastfeed. Cymbalta can pass into your breast milk. Talk to your healthcare provider about the best way to feed your baby while taking Cymbalta.

Tell your healthcare provider about all the medicines that you take, including prescription and over-the-counter medicines, vitamins, and herbal supplements. Cymbalta and some medicines may interact with each other, may not work as well, or may cause serious side effects.

Especially tell your healthcare provider if you take:

- triptans used to treat migraine headache
- medicines used to treat mood, anxiety, psychotic or thought disorders, including tricyclics, lithium, buspirone, SSRIs, SNRIs or MAOIs
- tramadol and fentanyl
- cimetidine
- the antibiotics ciprofloxacin, enoxacin
- medicine to treat irregular heart rate (like propafenone, flecainide, quinidine)
- theophylline
- the blood thinner warfarin (Coumadin, Jantoven)
- non-steroidal anti-inflammatory drug (NSAID) (like ibuprofen, naproxen or aspirin).
- over-the-counter supplements such as tryptophan or St. John’s Wort
- thioridazine (Mellaril). Mellaril together with Cymbalta can cause serious heart rhythm problems or sudden death.

Ask your healthcare provider for a list of these medicines if you are not sure.

Do not take Cymbalta with any other medicine that contain duloxetine.

How should I take Cymbalta?

- Take Cymbalta exactly as your healthcare provider tells you to take it. Your healthcare provider may need to change the dose of Cymbalta until it is the right dose for you.
- Swallow Cymbalta whole. Do not chew or crush Cymbalta.
- Do not open the capsule and sprinkle on food or mix with liquids. Opening the capsule may affect how well Cymbalta works.
- Cymbalta may be taken with or without food.
- If you miss a dose of Cymbalta, take the missed dose as soon as you remember. If it is almost time for the next dose, skip the missed dose and take your next dose at the regular time. Do not take two doses of Cymbalta at the same time.
- If you take too much Cymbalta, call your healthcare provider or poison control center at 1-800-222-1222 right away, or get emergency treatment.
- When switching from another antidepressant to Cymbalta your healthcare provider may want to lower the dose of the initial antidepressant first to potentially avoid side effects.

What should I avoid while taking Cymbalta?

- Cymbalta can cause sleepiness or may affect your ability to make decisions, think clearly, or react quickly. You should not drive, operate heavy machinery, or do other dangerous activities until you know how Cymbalta affects you.
- Use of Cymbalta concomitantly with heavy alcohol intake may be associated with severe liver injury. Avoid heavy alcohol use while taking Cymbalta.

What are the possible side effects of Cymbalta?

Cymbalta may cause serious side effects, including: See “What is the most important information I should know about Cymbalta?”

Common possible side effects in people who take Cymbalta include:

1. liver damage. Symptoms may include:

- itching
- right upper abdominal pain
- dark urine
- yellow skin or eyes
- enlarged liver
- increased liver enzymes

2. changes in blood pressure and falls. Monitor your blood pressure before starting and throughout treatment. Cymbalta may:

- increase your blood pressure.
- decrease your blood pressure when standing and cause dizziness or fainting, mostly when first starting Cymbalta or when increasing the dose.
- increase risk of falls, especially in elderly.

3. Serotonin Syndrome: This condition can be life-threatening and symptoms may include:

- agitation, hallucinations, coma or other changes in mental status
- coordination problems or muscle twitching (overactive reflexes)
- racing heartbeat, high or low blood pressure
- sweating or fever
- nausea, vomiting, or diarrhea
- muscle rigidity
- dizziness
- flushing
- tremor
- seizures

4. abnormal bleeding: Cymbalta and other antidepressant medicines may increase your risk of bleeding or bruising, especially if you take the blood thinner warfarin (Coumadin, Jantoven), a non-steroidal anti-inflammatory drug (NSAIDs, like ibuprofen or naproxen), or aspirin.

5. severe skin reactions: Cymbalta may cause serious skin reactions that may require stopping its use. This may need to be treated in a hospital and may be life-threatening. Call your healthcare provider right away or get emergency help if you have skin blisters, peeling rash, sores in the mouth, hives or any other allergic reactions.

6. discontinuation symptoms: Do not stop Cymbalta without first talking to your healthcare provider. Stopping Cymbalta too quickly or changing from another antidepressant too quickly may result in serious symptoms including:

- anxiety
- irritability
- feeling tired or problems sleeping
- headache
- sweating
- dizziness
- electric shock-like sensations
- vomiting or nausea
- diarrhea

7. manic episodes:

- greatly increased energy
- severe trouble sleeping
- racing thoughts
- reckless behavior
- unusually grand ideas
- excessive happiness or irritability
- talking more or faster than usual

8. visual problems:

- eye pain
- changes in vision
- swelling or redness in or around the eye

Only some people are at risk for these problems. You may want to undergo an eye examination to see if you are at risk and receive preventative treatment if you are.

9. seizures or convulsions

10. low salt (sodium) levels in the blood. Elderly people may be at greater risk for this. Symptoms may include:

- headache
- weakness or feeling unsteady
- confusion, problems concentrating or thinking or memory problems

11. problems with urination. Symptoms may include:

- decreased urine flow
- unable to pass any urine

The most common side effects of Cymbalta include:

- nausea
- dry mouth
- sleepiness
- fatigue
- constipation
- loss of appetite
- increased sweating
- dizziness

Common possible side effects in children and adolescents who take Cymbalta include:

- nausea
- decreased weight
- dizziness

Side effects in adults may also occur in children and adolescents who take Cymbalta. Children and adolescents should have height and weight monitored during treatment.

Tell your healthcare provider if you have any side effect that bothers you or that does not go away. These are not all the possible side effects of Cymbalta. For more information, ask your healthcare provider or pharmacist.

Call your doctor for medical advice about side effects. You may report side effects to 1-800-FDA-1088.

How should I store Cymbalta?

Store Cymbalta at room temperature between 68°F to 77°F (20°C to 25°C).

Keep Cymbalta and all medicines out of the reach of children.

General information about the safe and effective use of Cymbalta.

Medicines are sometimes prescribed for purposes other than those listed in a Medication Guide. Do not use Cymbalta for a condition for which it was not prescribed. Do not give Cymbalta to other people, even if they have the same symptoms that you have. It may harm them.

This Medication Guide summarizes the most important information about Cymbalta. If you would like more information, talk with your healthcare provider. You may ask your healthcare provider or pharmacist for information about Cymbalta that is written for healthcare professionals.

For more information, call 1-800-545-5979.

What are the ingredients in Cymbalta?

Active ingredient: duloxetine hydrochloride

Inactive ingredients:

FD&C Blue No. 2, gelatin, hypromellose, hydroxypropyl methylcellulose acetate succinate, sodium lauryl sulfate, sucrose, sugar spheres, talc, titanium dioxide, and triethyl citrate. The 20 and 60 mg capsules also contain iron oxide yellow.

This Medication Guide has been approved by the U.S. Food and Drug Administration.

Coumadin, Jantoven, and Mellaril are trademarks of their respective owners and not trademarks of Eli Lilly and Company.

Medication Guide revised: November 2014

Marketed by: Lilly USA, LLC
Indianapolis, IN 46285, USA

Cymbalta is a registered trademark of Eli Lilly and Company.

Copyright © 2009, 2014, Eli Lilly and Company. All rights reserved.

CYM-0003-MG-20141125